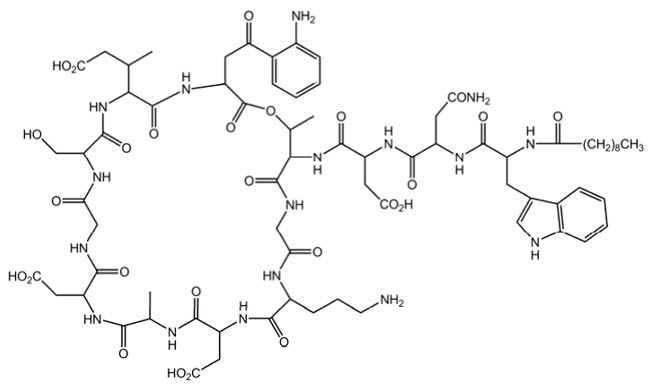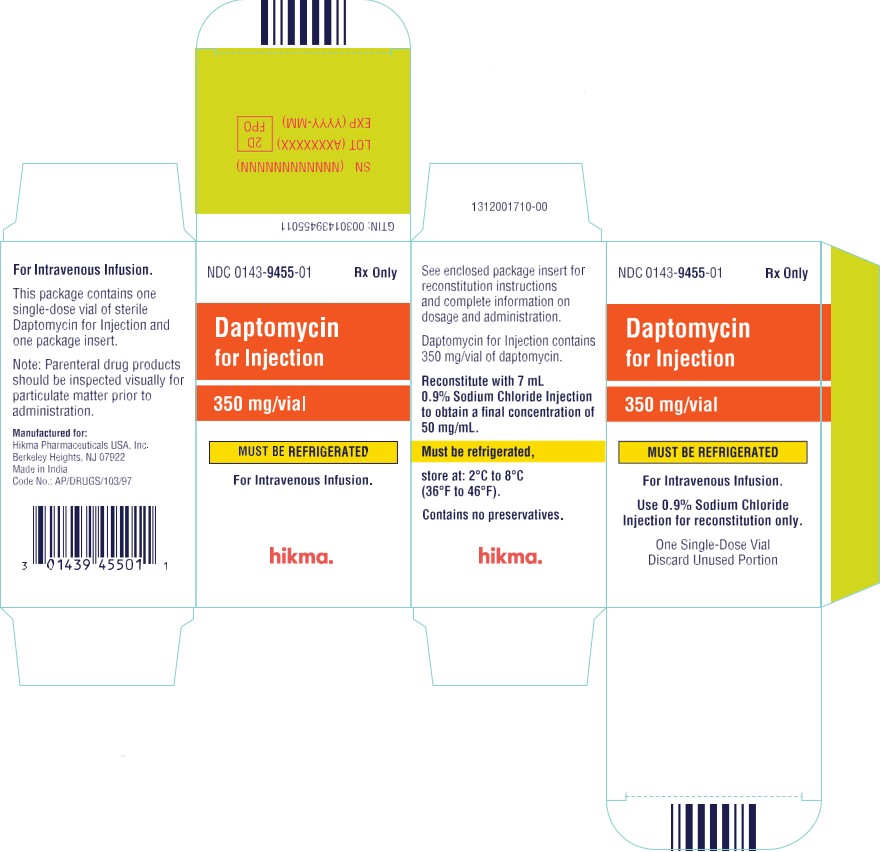 DRUG LABEL: Daptomycin
NDC: 0143-9455 | Form: INJECTION, POWDER, LYOPHILIZED, FOR SOLUTION
Manufacturer: Hikma Pharmaceuticals USA Inc.
Category: prescription | Type: HUMAN PRESCRIPTION DRUG LABEL
Date: 20260227

ACTIVE INGREDIENTS: DAPTOMYCIN 350 mg/7 mL
INACTIVE INGREDIENTS: SODIUM HYDROXIDE

HIGHLIGHTS OF PRESCRIBING INFORMATION

These highlights do not include all the information needed to use DAPTOMYCIN FOR INJECTION safely and effectively. See full prescribing information for DAPTOMYCIN FOR INJECTION.
DAPTOMYCIN for injection, for intravenous use
Initial U.S. Approval: 2003

RECENT MAJOR CHANGES

Dosage and Administration (2) | 10/2023

1 INDICATIONS AND USAGE

Daptomycin for Injection is a lipopeptide antibacterial indicated for the treatment of:

- Complicated skin and skin structure infections (cSSSI) in adult and pediatric patients (1 to 17 years of age) (1.1) and,
- Staphylococcus aureus bloodstream infections (bacteremia), in adult patients including those with right-sided infective endocarditis, (1.2)
- Staphylococcus aureus bloodstream infections (bacteremia) in pediatric patients (1 to 17 years of age). (1.3)

Limitations of Use:

- Daptomycin for Injection is not indicated for the treatment of pneumonia. (1.4)
- Daptomycin for Injection is not indicated for the treatment of left-sided infective endocarditis due to S. aureus. (1.4)
- Daptomycin for Injection is not recommended in pediatric patients younger than one year of age due to the risk of potential effects on muscular, neuromuscular, and/or nervous systems (either peripheral and/or central) observed in neonatal dogs. (1.4)

To reduce the development of drug-resistant bacteria and maintain the effectiveness of Daptomycin for Injection and other antibacterial drugs, Daptomycin for Injection should be used to treat or prevent infections that are proven or strongly suspected to be caused by bacteria. (1.5)

2 DOSAGE AND ADMINISTRATION

Adult Patients

- Administer to adult patients intravenously in 0.9% sodium chloride, either by injection over a 2-minute period or by infusion over a 30-minute period. (2.1, 2.7)
- Recommended dosage regimen for adult patients (2.2, 2.4, 2.6):

Creatinine Clearance (CLCR) | Dosage Regimen
Creatinine Clearance (CLCR) | cSSSI For 7 to 14 days | S. aureus Bacteremia For 2 to 6 weeks
≥30 mL/min | 4 mg/kg once every 24 hours | 6 mg/kg once every 24 hours
<30 mL/min, including hemodialysis and CAPD | 4 mg/kg once every 48 hours [Administered following hemodialysis on hemodialysis days.] | 6 mg/kg once every 48 hours

Pediatric Patients

- Unlike in adults, do NOT administer by injection over a two (2) minute period to pediatric patients. (2.1, 2.7)
- Administer to pediatric patients intravenously in 0.9% sodium chloride, by infusion over a 30- or 60-minute period, based on age. (2.1, 2.7)
- Recommended dosage regimen for pediatric patients (1 to 17 years of age) with cSSSI, based on age (2.3):

Age group | Dosage [Recommended dosage is for pediatric patients (1 to 17 years of age) with normal renal function. Dosage adjustment for pediatric patients with renal impairment has not been established.] | Duration of therapy
12 to 17 years | 5 mg/kg once every 24 hours infused over 30 minutes | Up to 14 days
7 to 11 years | 7 mg/kg once every 24 hours infused over 30 minutes | Up to 14 days
2 to 6 years | 9 mg/kg once every 24 hours infused over 60 minutes | Up to 14 days
1 to less than 2 years | 10 mg/kg once every 24 hours infused over 60 minutes | Up to 14 days

- Recommended dosage regimen for pediatric patients (1 to 17 years of age) with S. aureus bacteremia, based on age (2.5):

Age group | Dosage [Recommended dosage is for pediatric patients (1 to 17 years of age) with normal renal function. Dosage adjustment for pediatric patients with renal impairment has not been established.] | Duration of therapy
12 to 17 years | 7 mg/kg once every 24 hours infused over 30 minutes | Up to 42 days
7 to 11 years | 9 mg/kg once every 24 hours infused over 30 minutes | Up to 42 days
1 to 6 years | 12 mg/kg once every 24 hours infused over 60 minutes | Up to 42 days

- There are other formulations of daptomycin that have differences concerning storage and reconstitution. Carefully follow the reconstitution and storage procedures described in this labeling. (2.7)
- Do not use in conjunction with ReadyMED® elastomeric infusion pumps in adult and pediatric patients. (2.9)

3 DOSAGE FORMS AND STRENGTHS

For Injection: 350 mg lyophilized powder for reconstitution in a single-dose vial (3)

4 CONTRAINDICATIONS

- Known hypersensitivity to daptomycin (4)

5 WARNINGS AND PRECAUTIONS

- Anaphylaxis/hypersensitivity reactions (including life-threatening): Discontinue Daptomycin for Injection and treat signs/symptoms. (5.1)
- Myopathy and rhabdomyolysis: Monitor CPK levels and follow muscle pain or weakness; if elevated CPK or myopathy occurs, consider discontinuation of Daptomycin for Injection. (5.2)
- Eosinophilic pneumonia: Discontinue Daptomycin for Injection and consider treatment with systemic steroids. (5.3)
- Drug Reaction with Eosinophilia and Systemic Symptoms (DRESS): Discontinue Daptomycin for Injection and institute appropriate treatment. (5.4)
- Tubulointerstitial Nephritis (TIN): Discontinue Daptomycin for Injection and institute appropriate treatment. (5.5)
- Peripheral neuropathy: Monitor for neuropathy and consider discontinuation. (5.6)
- Potential nervous system and/or muscular system effects in pediatric patients younger than 12 months: Avoid use of Daptomycin for Injection in this age group. (5.7)
- Clostridioides difficile–associated diarrhea: Evaluate patients if diarrhea occurs. (5.8)
- Persisting or relapsing S. aureus bacteremia/endocarditis: Perform susceptibility testing and rule out sequestered foci of infection. (5.9)
- Decreased efficacy was observed in adult patients with moderate baseline renal impairment. (5.10)

6 ADVERSE REACTIONS

- Adult cSSSI Patients: The most common adverse reactions that occurred in ≥2% of adult cSSSI patients receiving daptomycin for injection 4 mg/kg were diarrhea, headache, dizziness, rash, abnormal liver function tests, elevated creatine phosphokinase (CPK), urinary tract infections, hypotension, and dyspnea. (6.1)
- Pediatric cSSSI Patients: The most common adverse reactions that occurred in ≥2% of pediatric patients receiving daptomycin for injection were diarrhea, vomiting, abdominal pain, pruritus, pyrexia, elevated CPK, and headache. (6.1)
- Adult S. aureus bacteremia/endocarditis Patients: The most common adverse reactions that occurred in ≥5% of S. aureus bacteremia/endocarditis patients receiving Daptomycin for Injection 6 mg/kg were sepsis, bacteremia, abdominal pain, chest pain, edema, pharyngolaryngeal pain, pruritus, increased sweating, insomnia, elevated CPK, and hypertension. (6.1)
- Pediatric S. aureus bacteremia Patients: The most common adverse reactions that occurred in ≥5% of pediatric patients receiving daptomycin for injection were vomiting and elevated CPK. (6.1)

To report SUSPECTED ADVERSE REACTIONS, contact Hikma Pharmaceuticals USA Inc. at 1-877-845-0689, or FDA at 1-800-FDA-1088 or www.fda.gov/medwatch.

FULL PRESCRIBING INFORMATION

1 INDICATIONS AND USAGE

1.1 Complicated Skin and Skin Structure Infections (cSSSI)

Daptomycin for Injection is indicated for the treatment of adult and pediatric patients (1 to 17 years of age) with complicated skin and skin structure infections (cSSSI) caused by susceptible isolates of the following Gram-positive bacteria: Staphylococcus aureus (including methicillin-resistant isolates), Streptococcus pyogenes, Streptococcus agalactiae, Streptococcus dysgalactiae subsp. equisimilis, and Enterococcus faecalis (vancomycin-susceptible isolates only).

1.2 Staphylococcus aureus Bloodstream Infections (Bacteremia) in Adult Patients, Including Those with Right-Sided Infective Endocarditis, Caused by Methicillin-Susceptible and Methicillin-Resistant Isolates

Daptomycin for Injection is indicated for the treatment of adult patients with Staphylococcus aureus bloodstream infections (bacteremia), including adult patients with right-sided infective endocarditis, caused by methicillin-susceptible and methicillin-resistant isolates.

1.3 Staphylococcus aureus Bloodstream Infections (Bacteremia) in Pediatric Patients (1 to 17 Years of Age)

Daptomycin for Injection is indicated for the treatment of pediatric patients (1 to 17 years of age) with Staphylococcus aureus bloodstream infections (bacteremia).

1.4 Limitations of Use

Daptomycin for Injection is not indicated for the treatment of pneumonia.

Daptomycin for Injection is not indicated for the treatment of left-sided infective endocarditis due to S. aureus. The clinical trial of daptomycin for injection in adult patients with S. aureus bloodstream infections included limited data from patients with left-sided infective endocarditis; outcomes in these patients were poor [see Clinical Studies (14.2)]. Daptomycin for Injection has not been studied in patients with prosthetic valve endocarditis.

Daptomycin for Injection is not recommended in pediatric patients younger than 1 year of age due to the risk of potential effects on muscular, neuromuscular, and/or nervous systems (either peripheral and/or central) observed in neonatal dogs [see Warnings and Precautions (5.7) and Nonclinical Toxicology (13.2)].

1.5 Usage

Appropriate specimens for microbiological examination should be obtained in order to isolate and identify the causative pathogens and to determine their susceptibility to daptomycin.

To reduce the development of drug-resistant bacteria and maintain the effectiveness of Daptomycin for Injection and other antibacterial drugs, Daptomycin for Injection should be used only to treat or prevent infections that are proven or strongly suspected to be caused by susceptible bacteria.

When culture and susceptibility information is available, it should be considered in selecting or modifying antibacterial therapy. In the absence of such data, local epidemiology and susceptibility patterns may contribute to the empiric selection of therapy. Empiric therapy may be initiated while awaiting test results.

2 DOSAGE AND ADMINISTRATION

2.1 Important Administration Duration Instructions

Adults

Administer the appropriate volume of the reconstituted Daptomycin for Injection (concentration of 50 mg/mL) to adult patients intravenously either by injection over a two (2) minute period or by intravenous infusion over a thirty (30) minute period [see Dosage and Administration (2.2, 2.4, 2.7)].

Pediatric Patients (1 to 17 Years of Age)

Unlike in adults, do NOT administer Daptomycin for Injection over a two (2) minute period to pediatric patients.

- Pediatric Patients 7 to 17 years of Age: Administer Daptomycin for Injection intravenously by infusion over a 30-minute period [see Dosage and Administration (2.3, 2.5, 2.7)].
- Pediatric Patients 1 to 6 years of Age: Administer Daptomycin for Injection intravenously by infusion over a 60-minute period [see Dosage and Administration (2.3, 2.5, 2.7)].

2.2 Dosage in Adults for cSSSI

Administer Daptomycin for Injection 4 mg/kg to adult patients intravenously in 0.9% sodium chloride injection once every 24 hours for 7 to 14 days.

2.3 Dosage in Pediatric Patients (1 to 17 Years of Age) for cSSSI

The recommended dosage regimens based on age for pediatric patients with cSSSI are shown in Table 1. Administer Daptomycin for Injection intravenously in 0.9% sodium chloride injection once every 24 hours for up to 14 days.

Table 1: Recommended Dosage of Daptomycin for Injection in Pediatric Patients (1 to 17 Years of Age) with cSSSI, Based on Age
Age Range | Dosage Regimen [Recommended dosage regimen is for pediatric patients (1 to 17 years of age) with normal renal function. Dosage adjustment for pediatric patients with renal impairment has not been established.] | Duration of therapy
12 to 17 years | 5 mg/kg once every 24 hours infused over 30 minutes
7 to 11 years | 7 mg/kg once every 24 hours infused over 30 minutes | Up to 14 days
2 to 6 years | 9 mg/kg once every 24 hours infused over 60 minutes
1 to less than 2 years | 10 mg/kg once every 24 hours infused over 60 minutes

2.4 Dosage in Adult Patients with Staphylococcus aureus Bloodstream Infections (Bacteremia), Including Those with Right-Sided Infective Endocarditis, Caused by Methicillin-Susceptible and Methicillin-Resistant Isolates

Administer Daptomycin for Injection 6 mg/kg to adult patients intravenously in 0.9% sodium chloride injection once every 24 hours for 2 to 6 weeks. There are limited safety data for the use of daptomycin for injection for more than 28 days of therapy. In the Phase 3 trial, there were a total of 14 adult patients who were treated with daptomycin for injection for more than 28 days.

2.5 Dosage in Pediatric Patients (1 to 17 Years of Age) with Staphylococcus aureus Bloodstream Infections (Bacteremia)

The recommended dosage regimens based on age for pediatric patients with S. aureus bloodstream infections (bacteremia) are shown in Table 2. Administer Daptomycin for Injection intravenously in 0.9% sodium chloride injection once every 24 hours for up to 42 days.

Table 2: Recommended Dosage of Daptomycin for Injection in Pediatric Patients (1 to 17 Years of Age) with S. aureus Bacteremia, Based on Age
Age group | Dosage [Recommended dosage is for pediatric patients (1 to 17 years of age) with normal renal function. Dosage adjustment for pediatric patients with renal impairment has not been established.] | Duration of therapy
12 to 17 years | 7 mg/kg once every 24 hours infused over 30 minutes
7 to 11 years | 9 mg/kg once every 24 hours infused over 30 minutes | Up to 42 days
1 to 6 years | 12 mg/kg once every 24 hours infused over 60 minutes | Up to 42 days

2.6 Dosage in Patients with Renal Impairment

Adult Patients:

No dosage adjustment is required in adult patients with creatinine clearance (CLCR) greater than or equal to 30 mL/min. The recommended dosage regimen for Daptomycin for Injection in adult patients with CLCR less than 30 mL/min, including adult patients on hemodialysis or continuous ambulatory peritoneal dialysis (CAPD), is 4 mg/kg (cSSSI) or 6 mg/kg (S. aureus bloodstream infections) once every 48 hours (Table 3). When possible, Daptomycin for Injection should be administered following the completion of hemodialysis, on hemodialysis days [see Warnings and Precautions (5.2, 5.10), Use in Specific Populations (8.6), and Clinical Pharmacology (12.3)].

Table 3: Recommended Dosage of Daptomycin for Injection in Adult Patients
Creatinine Clearance (CLCR) | Dosage Regimen in Adults
Creatinine Clearance (CLCR) | cSSSI | S. aureus Bloodstream Infections
Greater than or equal to 30 mL/min | 4 mg/kg once every 24 hours | 6 mg/kg once every 24 hours
Less than 30 mL/min, including hemodialysis and CAPD | 4 mg/kg once every 48 hours [When possible, administer Daptomycin for Injection following the completion of hemodialysis, on hemodialysis days.] | 6 mg/kg once every 48 hours

Pediatric Patients:

The dosage regimen for Daptomycin for Injection in pediatric patients with renal impairment has not been established.

2.7 Preparation and Administration of Daptomycin for Injection

There are other formulations of daptomycin that have differences concerning reconstitution and storage. Carefully follow the reconstitution and storage procedures described in this labeling.

Reconstitution of Daptomycin for Injection Vial

Daptomycin for Injection is supplied in single-dose vials, each containing 350 mg daptomycin as a sterile, lyophilized powder. The contents of a Daptomycin for Injection vial should be reconstituted with 0.9% sodium chloride injection, using aseptic technique, to 50 mg/mL as follows:

1. To minimize foaming, AVOID vigorous agitation or shaking of the vial during or after reconstitution.
2. Remove the polypropylene flip-off cap from the Daptomycin for Injection vial to expose the central portion of the rubber stopper.
3. Wipe the top of the rubber stopper with an alcohol swab or other antiseptic solution and allow to dry. After cleaning, do not touch the rubber stopper or allow it to touch any other surface.
4. Slowly transfer 7 mL of 0.9% sodium chloride injection through the center of the rubber stopper into the Daptomycin for Injection vial, pointing the transfer needle toward the wall of the vial. It is recommended that a beveled sterile transfer needle that is 21 gauge or smaller in diameter, or a needleless device is used, pointing the transfer needle toward the wall of the vial.
5. Ensure that all of the Daptomycin for Injection powder is wetted by gently rotating the vial.
  1. Allow the wetted product to stand undisturbed for 10 minutes.
  2. Gently rotate or swirl the vial contents for a few minutes, as needed, to obtain a completely reconstituted solution.

Administration Instructions

Parenteral drug products should be inspected visually for particulate matter prior to administration. Slowly remove reconstituted liquid (50 mg daptomycin/mL) from the vial using a beveled sterile needle that is 21 gauge or smaller in diameter. Administer as an intravenous injection or infusion as described below:

Adults

Intravenous Injection over a period of 2 minutes

- For intravenous (IV) injection over a period of 2 minutes in adult patients only: Administer the appropriate volume of the reconstituted Daptomycin for Injection (concentration of 50 mg/mL).

Intravenous Infusion over a period of 30 minutes

- For IV infusion over a period of 30 minutes in adult patients: The appropriate volume of the reconstituted Daptomycin for Injection (concentration of 50 mg/mL) should be further diluted, using aseptic technique, into a 50 mL IV infusion bag containing 0.9% sodium chloride injection.

Pediatric Patients (1 to 17 Years of Age)

Intravenous Infusion over a period of 30 or 60 minutes

- Unlike in Adults, do NOT administer Daptomycin for Injection by injection over a two (2) minute period to pediatric patients [see Dosage and Administration (2.1)].
- For Intravenous infusion over a period of 60 minutes in pediatric patients 1 to 6 years of age: The appropriate volume of the reconstituted Daptomycin for Injection (concentration of 50 mg/mL) should be further diluted, using aseptic technique, into an intravenous infusion bag containing 25 mL of 0.9% sodium chloride injection. The infusion rate should be maintained at 0.42 mL/minute over the 60-minute period.
- For Intravenous infusion over a period of 30 minutes in pediatric patients 7 to 17 years of age: The appropriate volume of the reconstituted Daptomycin for Injection (concentration of 50 mg/mL) should be further diluted, using aseptic technique, into a 50 mL IV infusion bag containing 0.9% sodium chloride injection. The infusion rate should be maintained at 1.67 mL/minute over the 30-minute period.

No preservative or bacteriostatic agent is present in this product. Aseptic technique must be used in the preparation of final IV solution. Do not exceed the In-Use storage conditions of the reconstituted and diluted solutions of Daptomycin for Injection described below. Discard unused portions of Daptomycin for Injection.

In-Use Storage Conditions for Daptomycin for Injection Once Reconstituted in Acceptable Intravenous Diluents

Stability studies have shown that the reconstituted solution is stable in the vial for 12 hours at room temperature and up to 48 hours if stored under refrigeration at 2°C to 8°C (36°F to 46°F).

The diluted solution is stable in the infusion bag for 12 hours at room temperature and 48 hours if stored under refrigeration. The combined storage time (reconstituted solution in vial and diluted solution in infusion bag) should not exceed 12 hours at room temperature or 48 hours under refrigeration.

2.8 Compatible Intravenous Solution for Reconstitution and Dilution

Daptomycin for Injection is compatible with 0.9% sodium chloride injection for reconstitution.

Reconstituted Daptomycin for injection can only be diluted with 0.9% sodium chloride injection.

2.9 Incompatibilities

Daptomycin for injection is not compatible with dextrose-containing diluents.

Daptomycin for Injection should not be used in conjunction with ReadyMED® elastomeric infusion pumps. Stability studies of daptomycin for injection solutions stored in ReadyMED® elastomeric infusion pumps identified an impurity (2-mercaptobenzothiazole) leaching from this pump system into the daptomycin for injection solution.

Because only limited data are available on the compatibility of daptomycin for injection with other IV substances, additives and other medications should not be added to Daptomycin for Injection single-dose vials or infusion bags, or infused simultaneously with Daptomycin for Injection through the same IV line. If the same IV line is used for sequential infusion of different drugs, the line should be flushed with a compatible intravenous solution before and after infusion with Daptomycin for Injection.

3 DOSAGE FORMS AND STRENGTHS

For Injection: 350 mg daptomycin as a sterile, pale yellow to light brown lyophilized powder for reconstitution in a single-dose vial.

4 CONTRAINDICATIONS

Daptomycin for Injection is contraindicated in patients with known hypersensitivity to daptomycin [see Warnings and Precautions (5.1)].

5 WARNINGS AND PRECAUTIONS

5.1 Anaphylaxis/Hypersensitivity Reactions

Anaphylaxis/hypersensitivity reactions have been reported with the use of antibacterial agents, including daptomycin for injection, and may be life-threatening. If an allergic reaction to Daptomycin for Injection occurs, discontinue the drug and institute appropriate therapy [see Adverse Reactions (6.2)].

5.2 Myopathy and Rhabdomyolysis

Myopathy, defined as muscle aching or muscle weakness in conjunction with increases in creatine phosphokinase (CPK) values to greater than 10 times the upper limit of normal (ULN), has been reported with the use of daptomycin for injection. Rhabdomyolysis, with or without acute renal failure, has been reported [see Adverse Reactions (6.2)].

Patients receiving Daptomycin for Injection should be monitored for the development of muscle pain or weakness, particularly of the distal extremities. In patients who receive Daptomycin for Injection, CPK levels should be monitored weekly, and more frequently in patients who received recent prior or concomitant therapy with an HMG-CoA reductase inhibitor or in whom elevations in CPK occur during treatment with Daptomycin for Injection.

In adult patients with renal impairment, both renal function and CPK should be monitored more frequently than once weekly [see Use in Specific Populations (8.6) and Clinical Pharmacology (12.3)].

In Phase 1 studies and Phase 2 clinical trials in adults, CPK elevations appeared to be more frequent when daptomycin for injection was dosed more than once daily. Therefore, Daptomycin for Injection should not be dosed more frequently than once a day.

Daptomycin for Injection should be discontinued in patients with unexplained signs and symptoms of myopathy in conjunction with CPK elevations to levels >1,000 U/L (~5× ULN), and in patients without reported symptoms who have marked elevations in CPK, with levels >2,000 U/L (≥10× ULN). In addition, consideration should be given to suspending agents associated with rhabdomyolysis, such as HMG-CoA reductase inhibitors, temporarily in patients receiving Daptomycin for Injection [see Drug Interactions (7.1)].

5.3 Eosinophilic Pneumonia

Eosinophilic pneumonia has been reported in patients receiving daptomycin for injection [see Adverse Reactions (6.2)]. In reported cases associated with daptomycin for injection, patients developed fever, dyspnea with hypoxic respiratory insufficiency, and diffuse pulmonary infiltrates or organizing pneumonia. In general, patients developed eosinophilic pneumonia 2 to 4 weeks after starting daptomycin for injection and improved when daptomycin for injection was discontinued and steroid therapy was initiated. Recurrence of eosinophilic pneumonia upon re-exposure has been reported. Patients who develop these signs and symptoms while receiving Daptomycin for Injection should undergo prompt medical evaluation, and Daptomycin for Injection should be discontinued immediately. Treatment with systemic steroids is recommended.

5.4 Drug Reaction with Eosinophilia and Systemic Symptoms (DRESS)

DRESS has been reported in post-marketing experience with daptomycin for injection [see Adverse Reactions (6.2)]. Patients who develop skin rash, fever, peripheral eosinophilia, and systemic organ (for example, hepatic, renal, pulmonary) impairment while receiving Daptomycin for Injection should undergo medical evaluation. If DRESS is suspected, discontinue Daptomycin for Injection promptly and institute appropriate treatment.

5.5 Tubulointerstitial Nephritis (TIN)

TIN has been reported in post-marketing experience with daptomycin for injection [see Adverse Reactions (6.2)]. Patients who develop new or worsening renal impairment while receiving Daptomycin for Injection should undergo medical evaluation. If TIN is suspected, discontinue Daptomycin for Injection promptly and institute appropriate treatment.

5.6 Peripheral Neuropathy

Cases of peripheral neuropathy have been reported during the daptomycin for injection postmarketing experience [see Adverse Reactions (6.2)]. Therefore, physicians should be alert to signs and symptoms of peripheral neuropathy in patients receiving Daptomycin for Injection. Monitor for neuropathy and consider discontinuation.

5.7 Potential Nervous System and/or Muscular System Effects in Pediatric Patients Younger than 12 Months

Avoid use of Daptomycin for Injection in pediatric patients younger than 12 months due to the risk of potential effects on muscular, neuromuscular, and/or nervous systems (either peripheral and/or central) observed in neonatal dogs with intravenous daptomycin [see Nonclinical Toxicology (13.2)].

5.8 Clostridioides difficile–Associated Diarrhea

Clostridioides difficile–associated diarrhea (CDAD) has been reported with the use of nearly all systemic antibacterial agents, including daptomycin for injection, and may range in severity from mild diarrhea to fatal colitis [see Adverse Reactions (6.2)]. Treatment with antibacterial agents alters the normal flora of the colon, leading to overgrowth of C. difficile.

C. difficile produces toxins A and B, which contribute to the development of CDAD.

Hypertoxin-producing strains of C. difficile cause increased morbidity and mortality, since these infections can be refractory to antimicrobial therapy and may require colectomy. CDAD must be considered in all patients who present with diarrhea following antibacterial use. Careful medical history is necessary because CDAD has been reported to occur more than 2 months after the administration of antibacterial agents.

If CDAD is suspected or confirmed, ongoing antibacterial use not directed against C. difficile may need to be discontinued. Appropriate fluid and electrolyte management, protein supplementation, antibacterial treatment of C. difficile, and surgical evaluation should be instituted as clinically indicated.

5.9 Persisting or Relapsing S. aureus Bacteremia/Endocarditis

Patients with persisting or relapsing S. aureus bacteremia/endocarditis or poor clinical response should have repeat blood cultures. If a blood culture is positive for S. aureus, minimum inhibitory concentration (MIC) susceptibility testing of the isolate should be performed using a standardized procedure, and diagnostic evaluation of the patient should be performed to rule out sequestered foci of infection. Appropriate surgical intervention (e.g., debridement, removal of prosthetic devices, valve replacement surgery) and/or consideration of a change in antibacterial regimen may be required.

Failure of treatment due to persisting or relapsing S. aureus bacteremia/endocarditis may be due to reduced daptomycin susceptibility (as evidenced by increasing MIC of the S. aureus isolate) [see Clinical Studies (14.2)].

5.10 Decreased Efficacy in Patients with Moderate Baseline Renal Impairment

Limited data are available from the two Phase 3 complicated skin and skin structure infection (cSSSI) trials regarding clinical efficacy of daptomycin for injection treatment in adult patients with creatinine clearance (CLCR) <50 mL/min; only 31/534 (6%) patients treated with daptomycin for injection in the intent-to-treat (ITT) population had a baseline CLCR <50 mL/min. Table 4 shows the number of adult patients by renal function and treatment group who were clinical successes in the Phase 3 cSSSI trials.

Table 4: Clinical Success Rates by Renal Function and Treatment Group in Phase 3 cSSSI Trials in Adult Patients (Population: ITT)
CLCR | Success Rate n/N (%)
CLCR | Daptomycin for Injection 4 mg/kg every 24h | Comparator
50–70 mL/min | 25/38 (66%) | 30/48 (63%)
30–<50 mL/min | 7/15 (47%) | 20/35 (57%)

In a subgroup analysis of the ITT population in the Phase 3 S. aureus bacteremia/endocarditis trial, clinical success rates, as determined by a treatment-blinded Adjudication Committee [see Clinical Studies (14.2)], in the daptomycin for injection-treated adult patients were lower in patients with baseline CLCR <50 mL/min (see Table 5). A decrease of the magnitude shown in Table 5 was not observed in comparator-treated patients.

Table 5: Adjudication Committee Clinical Success Rates at Test of Cure by Baseline Creatinine Clearance and Treatment Subgroup in the S. aureus Bacteremia/Endocarditis Trial in Adult Patients (Population: ITT)
Baseline CLCR | Success Rate n/N (%)
Baseline CLCR | Daptomycin for Injection 6 mg/kg every 24h |  | Comparator
Baseline CLCR | Bacteremia | Right-Sided Infective Endocarditis | Bacteremia | Right-Sided Infective Endocarditis
>80 mL/min | 30/50 (60%) | 7/14 (50%) | 19/42 (45%) | 5/11 (46%)
50–80 mL/min | 12/26 (46%) | 1/4 (25%) | 13/31 (42%) | 1/2 (50%)
30–<50 mL/min | 2/14 (14%) | 0/1 (0%) | 7/17 (41%) | 1/1 (100%)

Consider these data when selecting antibacterial therapy for use in adult patients with baseline moderate to severe renal impairment.

5.11 Increased International Normalized Ratio (INR)/Prolonged Prothrombin Time

Clinically relevant plasma concentrations of daptomycin have been observed to cause a significant concentration-dependent false prolongation of prothrombin time (PT) and elevation of International Normalized Ratio (INR) when certain recombinant thromboplastin reagents are utilized for the assay [see Drug Interactions (7.2)].

5.12 Development of Drug-Resistant Bacteria

Prescribing Daptomycin for Injection in the absence of a proven or strongly suspected bacterial infection or a prophylactic indication is unlikely to provide benefit to the patient and increases the risk of the development of drug-resistant bacteria.

6 ADVERSE REACTIONS

The following adverse reactions are described, or described in greater detail, in other sections:

- Anaphylaxis/Hypersensitivity Reactions [see Warnings and Precautions (5.1)]
- Myopathy and Rhabdomyolysis [see Warnings and Precautions (5.2)]
- Eosinophilic Pneumonia [see Warnings and Precautions (5.3)]
- Drug Reaction with Eosinophilia and Systemic Symptoms [see Warnings and Precautions (5.4)]
- Tubulointerstitial Nephritis [see Warnings and Precautions (5.5)]
- Peripheral Neuropathy [see Warnings and Precautions (5.6)]
- Increased International Normalized Ratio (INR)/Prolonged Prothrombin Time [see Warnings and Precautions (5.11) and Drug Interactions (7.2)]

6.1 Clinical Trials Experience

Because clinical trials are conducted under widely varying conditions, adverse reaction rates observed in the clinical trials of a drug cannot be directly compared with rates in the clinical trials of another drug and may not reflect the rates observed in practice.

Clinical Trial Experience in Adult Patients

Clinical trials enrolled 1,864 adult patients treated with daptomycin for injection and 1,416 treated with comparator.

Complicated Skin and Skin Structure Infection Trials in Adults

In Phase 3 complicated skin and skin structure infection (cSSSI) trials in adult patients, daptomycin for injection was discontinued in 15/534 (2.8%) patients due to an adverse reaction, while comparator was discontinued in 17/558 (3.0%) patients.

The rates of the most common adverse reactions, organized by body system, observed in adult patients with cSSSI (receiving 4 mg/kg daptomycin for injection) are displayed in Table 6.

Table 6: Incidence of Adverse Reactions that Occurred in ≥2% of Adult Patients in the Daptomycin for Injection Treatment Group and ≥ the Comparator Treatment Group in Phase 3 cSSSI Trials
Adverse Reaction | Adult Patients (%)
Adverse Reaction | Daptomycin for Injection 4 mg/kg (N=534) | Comparator [Comparator: vancomycin (1 g IV q12h) or an anti-staphylococcal semi-synthetic penicillin (i.e., nafcillin, oxacillin, cloxacillin, or flucloxacillin; 4 to 12 g/day IV in divided doses).] (N=558)
Gastrointestinal disorders
Diarrhea | 5.2 | 4.3
Nervous system disorders
Headache | 5.4 | 5.4
Dizziness | 2.2 | 2.0
Skin/subcutaneous disorders
Rash | 4.3 | 3.8
Diagnostic investigations
Abnormal liver function tests | 3.0 | 1.6
Elevated CPK | 2.8 | 1.8
Infections
Urinary tract infections | 2.4 | 0.5
Vascular disorders
Hypotension | 2.4 | 1.4
Respiratory disorders
Dyspnea | 2.1 | 1.6

Drug-related adverse reactions (possibly or probably drug-related) that occurred in <1% of adult patients receiving daptomycin for injection in the cSSSI trials are as follows:

Body as a Whole: fatigue, weakness, rigors, flushing, hypersensitivity

Blood/Lymphatic System: leukocytosis, thrombocytopenia, thrombocytosis, eosinophilia, increased International Normalized Ratio (INR)

Cardiovascular System: supraventricular arrhythmia

Dermatologic System: eczema

Digestive System: abdominal distension, stomatitis, jaundice, increased serum lactate dehydrogenase

Metabolic/Nutritional System: hypomagnesemia, increased serum bicarbonate, electrolyte disturbance

Musculoskeletal System: myalgia, muscle cramps, muscle weakness, arthralgia

Nervous System: vertigo, mental status change, paresthesia

Special Senses: taste disturbance, eye irritation

S. aureus Bacteremia/Endocarditis Trial in Adults

In the S. aureus bacteremia/endocarditis trial involving adult patients, daptomycin for injection was discontinued in 20/120 (16.7%) patients due to an adverse reaction, while comparator was discontinued in 21/116 (18.1%) patients.

Serious Gram-negative infections (including bloodstream infections) were reported in 10/120 (8.3%) daptomycin for injection-treated patients and 0/115 comparator-treated patients. Comparator-treated patients received dual therapy that included initial gentamicin for 4 days. Infections were reported during treatment and during early and late follow-up. Gram-negative infections included cholangitis, alcoholic pancreatitis, sternal osteomyelitis/mediastinitis, bowel infarction, recurrent Crohn's disease, recurrent line sepsis, and recurrent urosepsis caused by a number of different Gram-negative bacteria.

The rates of the most common adverse reactions, organized by System Organ Class (SOC), observed in adult patients with S. aureus bacteremia/endocarditis (receiving 6 mg/kg daptomycin for injection) are displayed in Table 7.

Table 7: Incidence of Adverse Reactions that Occurred in ≥5% of Adult Patients in the Daptomycin for Injection Treatment Group and ≥ the Comparator Treatment Group in the S. aureus Bacteremia/Endocarditis Trial
Adverse Reaction [NOS, not otherwise specified.] | Adult Patients n (%)
Adverse Reaction [NOS, not otherwise specified.] | Daptomycin for Injection 6 mg/kg (N=120) | Comparator [Comparator: vancomycin (1 g IV q12h) or an anti-staphylococcal semi-synthetic penicillin (i.e., nafcillin, oxacillin, cloxacillin, or flucloxacillin; 2 g IV q4h), each with initial low-dose gentamicin.] (N=116)
Infections and infestations
Sepsis NOS | 6 (5%) | 3 (3%)
Bacteremia | 6 (5%) | 0 (0%)
Gastrointestinal disorders
Abdominal pain NOS | 7 (6%) | 4 (3%)
General disorders and administration site conditions
Chest pain | 8 (7%) | 7 (6%)
Edema NOS | 8 (7%) | 5 (4%)
Respiratory, thoracic and mediastinal disorders
Pharyngolaryngeal pain | 10 (8%) | 2 (2%)
Skin and subcutaneous tissue disorders
Pruritus | 7 (6%) | 6 (5%)
Sweating increased | 6 (5%) | 0 (0%)
Psychiatric disorders
Insomnia | 11 (9%) | 8 (7%)
Investigations
Blood creatine phosphokinase increased | 8 (7%) | 1 (1%)
Vascular disorders
Hypertension NOS | 7 (6%) | 3 (3%)

The following reactions, not included above, were reported as possibly or probably drug-related in the daptomycin for injection-treated group:

Blood and Lymphatic System Disorders: eosinophilia, lymphadenopathy, thrombocythemia, thrombocytopenia

Cardiac Disorders: atrial fibrillation, atrial flutter, cardiac arrest

Ear and Labyrinth Disorders: tinnitus

Eye Disorders: vision blurred

Gastrointestinal Disorders: dry mouth, epigastric discomfort, gingival pain, hypoesthesia oral

Infections and Infestations: candidal infection NOS, vaginal candidiasis, fungemia, oral candidiasis, urinary tract infection fungal

Investigations: blood phosphorous increased, blood alkaline phosphatase increased, INR increased, liver function test abnormal, alanine aminotransferase increased, aspartate aminotransferase increased, prothrombin time prolonged

Metabolism and Nutrition Disorders: appetite decreased NOS

Musculoskeletal and Connective Tissue Disorders: myalgia

Nervous System Disorders: dyskinesia, paresthesia

Psychiatric Disorders: hallucination NOS

Renal and Urinary Disorders: proteinuria, renal impairment NOS

Skin and Subcutaneous Tissue Disorders: pruritus generalized, rash vesicular

Other Trials in Adults

In Phase 3 trials of community-acquired pneumonia (CAP) in adult patients, the death rate and rates of serious cardiorespiratory adverse events were higher in Daptomycin for Injection-treated patients than in comparator-treated patients. These differences were due to lack of therapeutic effectiveness of Daptomycin for Injection in the treatment of CAP in patients experiencing these adverse events [see Indications and Usage (1.4)].

Laboratory Changes in Adults

Complicated Skin and Skin Structure Infection Trials in Adults

In Phase 3 cSSSI trials of adult patients receiving Daptomycin for Injection at a dose of 4 mg/kg, elevations in CPK were reported as clinical adverse events in 15/534 (2.8%) Daptomycin for Injection-treated patients, compared with 10/558 (1.8%) comparator-treated patients. Of the 534 patients treated with Daptomycin for Injection, 1 (0.2%) had symptoms of muscle pain or weakness associated with CPK elevations to greater than 4 times the upper limit of normal (ULN). The symptoms resolved within 3 days and CPK returned to normal within 7 to 10 days after treatment was discontinued [see Warnings and Precautions (5.2)]. Table 8 summarizes the CPK shifts from Baseline through End of Therapy in the cSSSI adult trials.

Table 8: Incidence of CPK Elevations from Baseline during Therapy in Either the Daptomycin for Injection Treatment Group or the Comparator Treatment Group in Phase 3 cSSSI Adult Trials
Change in CPK |  | All Adult Patients |  |  |  | Adult Patients with Normal CPK at Baseline
Change in CPK |  | Daptomycin for Injection 4 mg/kg (N=430) |  | Comparator [Comparator: vancomycin (1 g IV q12h) or an anti-staphylococcal semi-synthetic penicillin (i.e., nafcillin, oxacillin, cloxacillin, or flucloxacillin; 4 to 12 g/day IV in divided doses).] (N=459) |  | Daptomycin for Injection 4 mg/kg (N=374) |  | Comparator (N=392)
Change in CPK |  | % | n | % | n | % | n | % | n
No Increase |  | 90.7 | 390 | 91.1 | 418 | 91.2 | 341 | 91.1 | 357
Maximum Value | >1× ULN [ULN (Upper Limit of Normal) is defined as 200 U/L.] | 9.3 | 40 | 8.9 | 41 | 8.8 | 33 | 8.9 | 35
 | >2× ULN | 4.9 | 21 | 4.8 | 22 | 3.7 | 14 | 3.1 | 12
 | >4× ULN | 1.4 | 6 | 1.5 | 7 | 1.1 | 4 | 1.0 | 4
 | >5× ULN | 1.4 | 6 | 0.4 | 2 | 1.1 | 4 | 0.0 | 0
 | >10× ULN | 0.5 | 2 | 0.2 | 1 | 0.2 | 1 | 0.0 | 0
Note: Elevations in CPK observed in adult patients treated with Daptomycin for Injection or comparator were not clinically or statistically significantly different.

S. aureus Bacteremia/Endocarditis Trial in Adults

In the S. aureus bacteremia/endocarditis trial in adult patients, at a dose of 6 mg/kg, 11/120 (9.2%) daptomycin for injection-treated patients, including two patients with baseline CPK levels >500 U/L, had CPK elevations to levels >500 U/L, compared with 1/116 (0.9%) comparator-treated patients. Of the 11 daptomycin for injection-treated patients, 4 had prior or concomitant treatment with an HMG-CoA reductase inhibitor. Three of these 11 daptomycin for injection-treated patients discontinued therapy due to CPK elevation, while the one comparator-treated patient did not discontinue therapy [see Warnings and Precautions (5.2)].

Clinical Trial Experience in Pediatric Patients

Complicated Skin and Skin Structure Infection Trial in Pediatric Patients

The safety of daptomycin for injection was evaluated in one clinical trial (in cSSSI), which included 256 pediatric patients (1 to 17 years of age) treated with intravenous daptomycin for injection and 133 patients treated with comparator agents. Patients were given age-dependent doses once daily for a treatment period of up to 14 days (median treatment period was 3 days). The doses given by age group were as follows: 10 mg/kg for 1 to <2 years, 9 mg/kg for 2 to 6 years, 7 mg/kg for 7 to 11 years and 5 mg/kg for 12 to 17 years of age [see Clinical Studies (14)]. Patients treated with daptomycin for injection were (51%) male, (49%) female and (46%) Caucasian and (32%) Asian.

Adverse Reactions Leading to Discontinuation

In the cSSSI study, daptomycin for injection was discontinued in 7/256 (2.7%) patients due to an adverse reaction, while comparator was discontinued in 7/133 (5.3%) patients.

Most Common Adverse Reactions

The rates of the most common adverse reactions, organized by body system, observed in these pediatric patients with cSSSI are displayed in Table 9.

Table 9: Adverse Reactions that Occurred in ≥2% of Pediatric Patients in the Daptomycin for Injection Treatment-Arm and Greater Than or Equal to the Comparator Treatment-Arm in the cSSSI Pediatric Trial
Adverse Reaction | Daptomycin for Injection (N = 256) | Comparator [Comparators included intravenous therapy with either vancomycin, clindamycin, or an anti-staphylococcal semi-synthetic penicillin (nafcillin, oxacillin or cloxacillin)] (N = 133)
Adverse Reaction | n (%) | n (%)
Gastrointestinal disorders
Diarrhea | 18 (7.0) | 7 (5.3)
Vomiting | 7 (2.7) | 1 (0.8)
Abdominal Pain | 5 (2.0) | 0
Skin and subcutaneous tissue disorders
Pruritus | 8 (3.1) | 2 (1.5)
General disorders and administration site conditions
Pyrexia | 10 (3.9) | 4 (3.0)
Investigations
Blood CPK increased | 14 (5.5) | 7 (5.3)
Nervous system disorders
Headache | 7 (2.7) | 3 (2.3)

The safety profile in the clinical trial of cSSSI pediatric patients was similar to that observed in the cSSSI adult patients.

S. aureus Bacteremia Trial in Pediatric Patients

The safety of daptomycin for injection was evaluated in one clinical trial (in S. aureus bacteremia), which treated 55 pediatric patients with intravenous daptomycin for injection and 26 patients with comparator agents. Patients were given age-dependent doses once daily for a treatment period of up to 42 days (mean duration of IV treatment was 12 days). The doses by age group were as follows: 12 mg/kg for 1 to <6 years, 9 mg/kg for 7 to 11 years and 7 mg/kg for 12 to 17 years of age [see Clinical Studies (14)]. Patients treated with daptomycin for injection were (69%) male and (31%) female. No patients 1 to <2 years of age were enrolled.

Adverse Reactions Leading to Discontinuation

In the bacteremia study, daptomycin for injection was discontinued in 3/55 (5.5%) patients due to an adverse reaction, while comparator was discontinued in 2/26 (7.7%) patients.

Most Common Adverse Reactions

The rates of the most common adverse reactions, organized by body system, observed in these pediatric patients with bacteremia are displayed in Table 10.

Table 10: Incidence of Adverse Reactions that Occurred in ≥5% of Pediatric Patients in the Daptomycin for Injection Treatment- Arm and Greater Than or Equal to the Comparator Treatment-Arm in the Pediatric Bacteremia Trial
Adverse Reaction | Daptomycin for Injection (N = 55) | Comparator [Comparators included intravenous therapy with either vancomycin, cefazolin, or an anti-staphylococcal semi-synthetic penicillin (nafcillin, oxacillin or cloxacillin)] (N = 26)
Adverse Reaction | n (%) | n (%)
Gastrointestinal disorders
Vomiting | 6 (10.9) | 2 (7.7)
Investigations
Blood CPK increased | 4 (7.3) | 0

6.2 Post-Marketing Experience

The following adverse reactions have been identified during post-approval use of daptomycin for injection. Because these reactions are reported voluntarily from a population of uncertain size, it is not always possible to reliably estimate their frequency or establish a causal relationship to drug exposure.

Blood and lymphatic system disorders: anemia, thrombocytopenia

General and administration site conditions: pyrexia

Immune System Disorders: anaphylaxis; hypersensitivity reactions, including angioedema, pruritus, hives, shortness of breath, difficulty swallowing, truncal erythema, and pulmonary eosinophilia [see Contraindications (4) and Warnings and Precautions (5.1)]

Infections and Infestations: Clostridioides difficile–associated diarrhea [see Warnings and Precautions (5.8)]

Laboratory Investigations: platelet count decreased

Musculoskeletal Disorders: myoglobin increased; rhabdomyolysis (some reports involved patients treated concurrently with Daptomycin for Injection and HMG-CoA reductase inhibitors) [see Warnings and Precautions (5.2), Drug Interactions (7.1), and Clinical Pharmacology (12.3)]

Respiratory, Thoracic, and Mediastinal Disorders: cough, eosinophilic pneumonia, organizing pneumonia [see Warnings and Precautions (5.3)]

Nervous System Disorders: peripheral neuropathy [see Warnings and Precautions (5.6)]

Skin and Subcutaneous Tissue Disorders: serious skin reactions, including drug reaction with eosinophilia and systemic symptoms (DRESS), vesiculobullous rash (with or without mucous membrane involvement, including Stevens-Johnson syndrome [SJS] and toxic epidermal necrolysis [TEN]), and acute generalized exanthematous pustulosis [see Warnings and Precautions (5.4)]

Gastrointestinal Disorders: nausea, vomiting

Renal and urinary disorders: acute kidney injury, renal insufficiency, renal failure and tubulointerstitial nephritis (TIN) [see Warnings and Precautions (5.5)]

Special Senses: visual disturbances

7 DRUG INTERACTIONS

7.1 HMG-CoA Reductase Inhibitors

In healthy adult subjects, concomitant administration of daptomycin for injection and simvastatin had no effect on plasma trough concentrations of simvastatin, and there were no reports of skeletal myopathy [see Clinical Pharmacology (12.3)].

However, inhibitors of HMG-CoA reductase may cause myopathy, which is manifested as muscle pain or weakness associated with elevated levels of creatine phosphokinase (CPK). In the adult Phase 3 S. aureus bacteremia/endocarditis trial, some patients who received prior or concomitant treatment with an HMG-CoA reductase inhibitor developed elevated CPK [see Adverse Reactions (6.1)]. Experience with the coadministration of HMG-CoA reductase inhibitors and daptomycin for injection in patients is limited; therefore, consideration should be given to suspending use of HMG-CoA reductase inhibitors temporarily in patients receiving Daptomycin for Injection.

7.2 Drug-Laboratory Test Interactions

Clinically relevant plasma concentrations of daptomycin have been observed to cause a significant concentration-dependent false prolongation of prothrombin time (PT) and elevation of International Normalized Ratio (INR) when certain recombinant thromboplastin reagents are utilized for the assay. The possibility of an erroneously elevated PT/INR result due to interaction with a recombinant thromboplastin reagent may be minimized by drawing specimens for PT or INR testing near the time of trough plasma concentrations of daptomycin. However, sufficient daptomycin concentrations may be present at trough to cause interaction.

If confronted with an abnormally high PT/INR result in a patient being treated with Daptomycin for Injection, it is recommended that clinicians:

1. Repeat the assessment of PT/INR, requesting that the specimen be drawn just prior to the next Daptomycin for Injection dose (i.e., at trough concentration). If the PT/INR value obtained at trough remains substantially elevated above what would otherwise be expected, consider evaluating PT/INR utilizing an alternative method.
2. Evaluate for other causes of abnormally elevated PT/INR results.

8 USE IN SPECIFIC POPULATIONS

8.1 Pregnancy

Risk Summary

Limited published data on use of daptomycin for injection in pregnant women are insufficient to inform a drug-associated risk for major birth defects and miscarriage. In animal reproduction studies performed in rats and rabbits daptomycin was administered intravenously during organogenesis at doses 2 and 4-times, respectively, the recommended 6 mg/kg human dose (on a body surface area basis). No evidence of adverse developmental outcomes was observed.

The background risk of major birth defects and miscarriage for the indicated population is unknown. All pregnancies have a background risk of birth defect, loss, or other adverse outcomes. In the U.S. general population, the estimated background risk of major birth defects and miscarriage in clinically recognized pregnancies is 2-4% and 15-20%, respectively.

Data

Animal Data

In pregnant rats, daptomycin was administered intravenously at doses of 5, 20, or 75 mg/kg/day during the gestation days 6 to 18. Maternal body weight gain was decreased at 75 mg/kg/day. No embryo/fetal effects were noted at the highest dose of 75 mg/kg/day, a dose approximately 2-fold higher than in humans at the recommended maximum dose of 6 mg/kg (based on body surface area).

In pregnant rabbits, daptomycin was administered intravenously at doses of 5, 20, or 75 mg/kg/day during the gestation days 6 to 15. Maternal body weight gain and food consumption were decreased at 75 mg/kg/day. No embryo/fetal effects were noted at the highest dose of 75 mg/kg/day, a dose approximately 4-fold higher than in humans at the maximum recommended dose of 6 mg/kg (based on body surface area).

In a combined fertility and pre/postnatal development study, daptomycin was administered intravenously to female rats at doses of 2, 25, 75 mg/kg/day from 14-days pre-mating through lactation/postpartum day 20. No effects on pre/postnatal development were observed up to the highest dose of 75 mg/kg/day, a dose approximately 2-fold higher than the maximum recommended human dose of 6 mg/kg (based on body surface area)^1.

8.2 Lactation

Risk Summary

Limited published data report that daptomycin is present in human milk at infant doses of 0.1% of the maternal dose (see Data)^2,3,4. There is no information on the effects of daptomycin on the breastfed infant or the effects of daptomycin on milk production. The developmental and health benefits of breastfeeding should be considered along with the mother's clinical need for Daptomycin for Injection and any potential adverse effects on the breastfed infant from Daptomycin for Injection or from the underlying maternal condition.

8.4 Pediatric Use

The safety and effectiveness of daptomycin for injection in the treatment of cSSSI and S. aureus bloodstream infections (bacteremia) have been established in the age groups 1 to 17 years of age. Use of daptomycin for injection in these age groups is supported by evidence from adequate and well-controlled studies in adults, with additional data from pharmacokinetic studies in pediatric patients, and from safety, efficacy and PK studies in pediatric patients with cSSSI and S. aureus bloodstream infections [see Adverse Reactions (6.1), Clinical Pharmacology (12.3), and Clinical Studies (14.1, 14.2)].

Safety and effectiveness of Daptomycin for Injection in pediatric patients below the age of one year have not been established. Avoid use of Daptomycin for Injection in pediatric patients younger than one year of age due to the risk of potential effects on muscular, neuromuscular, and/or nervous systems (either peripheral and/or central) observed in neonatal dogs [see Warnings and Precautions (5.7) and Nonclinical Toxicology (13.2)].

Daptomycin for Injection is not indicated in pediatric patients with renal impairment because dosage has not been established in these patients.

Daptomycin for Injection has not been studied in pediatric patients with other bacterial infections.

8.5 Geriatric Use

Of the 534 adult patients treated with daptomycin for injection in Phase 3 controlled clinical trials of complicated skin and skin structure infections (cSSSI), 27% were 65 years of age or older and 12% were 75 years of age or older. Of the 120 adult patients treated with daptomycin for injection in the Phase 3 controlled clinical trial of S. aureus bacteremia/endocarditis, 25% were 65 years of age or older and 16% were 75 years of age or older. In Phase 3 adult clinical trials of cSSSI and S. aureus bacteremia/endocarditis, clinical success rates were lower in patients ≥65 years of age than in patients <65 years of age. In addition, treatment-emergent adverse events were more common in patients ≥65 years of age than in patients <65 years of age.

The exposure of daptomycin was higher in healthy elderly subjects than in healthy young adult subjects. However, no adjustment of Daptomycin for Injection dosage is warranted for elderly patients with creatinine clearance (CLCR) ≥30 mL/min [see Dosage and Administration (2.6) and Clinical Pharmacology (12.3)].

8.6 Patients with Renal Impairment

Daptomycin is eliminated primarily by the kidneys; therefore, a modification of Daptomycin for Injection dosage interval is recommended for adult patients with CLCR <30 mL/min, including patients receiving hemodialysis or continuous ambulatory peritoneal dialysis (CAPD). In adult patients with renal impairment, both renal function and creatine phosphokinase (CPK) should be monitored more frequently than once weekly [see Dosage and Administration (2.6), Warnings and Precautions (5.2, 5.10), and Clinical Pharmacology (12.3)].

The dosage regimen for Daptomycin for Injection in pediatric patients with renal impairment has not been established.

10 OVERDOSAGE

In the event of overdosage, supportive care is advised with maintenance of glomerular filtration. Daptomycin is cleared slowly from the body by hemodialysis (approximately 15% of the administered dose is removed over 4 hours) and by peritoneal dialysis (approximately 11% of the administered dose is removed over 48 hours). The use of high-flux dialysis membranes during 4 hours of hemodialysis may increase the percentage of dose removed compared with that removed by low-flux membranes.

11 DESCRIPTION

Daptomycin for Injection contains daptomycin, a cyclic lipopeptide antibacterial agent derived from the fermentation of Streptomyces roseosporus. The chemical name is N-decanoyl-L-tryptophyl-D-asparaginyl-L-aspartyl-L-threonylglycyl-L-ornithyl-L-aspartyl-D-alanyl-L-aspartylglycyl-D-seryl-threo-3-methyl-L-glutamyl-3-anthraniloyl-L-alanine ε1-lactone. The chemical structure is:

The empirical formula is C72H101N17O26; the molecular weight is 1620.67. Daptomycin for Injection is supplied in a single-dose vial as a sterile, preservative-free, pale yellow to light brown, lyophilized cake containing approximately 350 mg of daptomycin for intravenous (IV) use following reconstitution with 0.9% sodium chloride injection [see Dosage and Administration (2.7)]. The only inactive ingredient is sodium hydroxide, which is used for pH adjustment. Freshly reconstituted solutions of Daptomycin for Injection range in color from pale yellow to light brown.

12 CLINICAL PHARMACOLOGY

12.1 Mechanism of Action

Daptomycin is an antibacterial drug [see Clinical Pharmacology (12.4)].

12.2 Pharmacodynamics

Based on animal models of infection, the antimicrobial activity of daptomycin appears to correlate with the AUC/MIC (area under the concentration-time curve/minimum inhibitory concentration) ratio for certain pathogens, including S. aureus. The principal pharmacokinetic/pharmacodynamic parameter best associated with clinical and microbiological cure has not been elucidated in clinical trials with daptomycin for injection.

12.3 Pharmacokinetics

Daptomycin for Injection Administered over a 30-Minute Period in Adults

The mean and standard deviation (SD) pharmacokinetic parameters of daptomycin at steady-state following intravenous (IV) administration of daptomycin for injection over a 30-minute period at 4 to 12 mg/kg every 24h to healthy young adults are summarized in Table 11.

Table 11: Mean (SD) Daptomycin Pharmacokinetic Parameters in Healthy Adult Volunteers at Steady-State
Dose [Daptomycin for injection was administered by IV infusion over a 30-minute period.] [Doses of daptomycin for injection in excess of 6 mg/kg have not been approved.] (mg/kg) |  | Pharmacokinetic Parameters [AUC0-24, area under the concentration-time curve from 0 to 24 hours; t1/2, elimination half-life; Vss, volume of distribution at steady-state; CLT, total plasma clearance; Cmax, maximum plasma concentration.]
Dose [Daptomycin for injection was administered by IV infusion over a 30-minute period.] [Doses of daptomycin for injection in excess of 6 mg/kg have not been approved.] (mg/kg) |  | AUC0-24 (mcg∙h/mL) | t1/2 (h) | Vss (L/kg) | CLT (mL/h/kg) | Cmax (mcg/mL)
4 | (N=6) | 494 (75) | 8.1 (1.0) | 0.096 (0.009) | 8.3 (1.3) | 57.8 (3.0)
6 | (N=6) | 632 (78) | 7.9 (1.0) | 0.101 (0.007) | 9.1 (1.5) | 93.9 (6.0)
8 | (N=6) | 858 (213) | 8.3 (2.2) | 0.101 (0.013) | 9.0 (3.0) | 123.3 (16.0)
10 | (N=9) | 1039 (178) | 7.9 (0.6) | 0.098 (0.017) | 8.8 (2.2) | 141.1 (24.0)
12 | (N=9) | 1277 (253) | 7.7 (1.1) | 0.097 (0.018) | 9.0 (2.8) | 183.7 (25.0)

Daptomycin pharmacokinetics were generally linear and time-independent at daptomycin for injection doses of 4 to 12 mg/kg every 24h administered by IV infusion over a 30-minute period for up to 14 days. Steady-state trough concentrations were achieved by the third daily dose. The mean (SD) steady-state trough concentrations attained following the administration of 4, 6, 8, 10, and 12 mg/kg every 24h were 5.9 (1.6), 6.7 (1.6), 10.3 (5.5), 12.9 (2.9), and 13.7 (5.2) mcg/mL, respectively.

Daptomycin for Injection Administered over a 2-Minute Period in Adults

Following IV administration of daptomycin for injection over a 2-minute period to healthy adult volunteers at doses of 4 mg/kg (N=8) and 6 mg/kg (N=12), the mean (SD) steady-state systemic exposure (AUC) values were 475 (71) and 701 (82) mcg∙h/mL, respectively. Values for maximum plasma concentration (Cmax) at the end of the 2-minute period could not be determined adequately in this study. However, using pharmacokinetic parameters from 14 healthy adult volunteers who received a single dose of daptomycin for injection 6 mg/kg IV administered over a 30-minute period in a separate study, steady-state Cmax values were simulated for Daptomycin for Injection 4 and 6 mg/kg IV administered over a 2-minute period. The simulated mean (SD) steady-state Cmax values were 77.7 (8.1) and 116.6 (12.2) mcg/mL, respectively.

Distribution

Daptomycin is reversibly bound to human plasma proteins, primarily to serum albumin, in a concentration-independent manner. The overall mean binding ranges from 90 to 93%.

In clinical studies, mean serum protein binding in adult subjects with creatinine clearance (CLCR) ≥30 mL/min was comparable to that observed in healthy adult subjects with normal renal function. However, there was a trend toward decreasing serum protein binding among subjects with CLCR <30 mL/min (88%), including those receiving hemodialysis (86%) and continuous ambulatory peritoneal dialysis (CAPD) (84%). The protein binding of daptomycin in adult subjects with moderate hepatic impairment (Child-Pugh Class B) was similar to that in healthy adult subjects.

The volume of distribution at steady-state (Vss) of daptomycin in healthy adult subjects was approximately 0.1 L/kg and was independent of dose.

Metabolism

In in vitro studies, daptomycin was not metabolized by human liver microsomes.

In 5 healthy adults after infusion of radiolabeled ^14C-daptomycin, the plasma total radioactivity was similar to the concentration determined by microbiological assay. Inactive metabolites were detected in urine, as determined by the difference between total radioactive concentrations and microbiologically active concentrations. In a separate study, no metabolites were observed in plasma on Day 1 following the administration of daptomycin for injection at 6 mg/kg to adult subjects. Minor amounts of three oxidative metabolites and one unidentified compound were detected in urine. The site of metabolism has not been identified.

Excretion

Daptomycin is excreted primarily by the kidneys. In a mass balance study of 5 healthy adult subjects using radiolabeled daptomycin, approximately 78% of the administered dose was recovered from urine based on total radioactivity (approximately 52% of the dose based on microbiologically active concentrations), and 5.7% of the administered dose was recovered from feces (collected for up to 9 days) based on total radioactivity.

Specific Populations

Patients with Renal Impairment

Population-derived pharmacokinetic parameters were determined for infected adult patients (complicated skin and skin structure infections [cSSSI] and S. aureus bacteremia) and noninfected adult subjects with various degrees of renal function (Table 12). Total plasma clearance (CLT), elimination half-life (t1/2), and volume of distribution at steady-state (Vss) in patients with cSSSI were similar to those in patients with S. aureus bacteremia. Following administration of daptomycin for injection 4 mg/kg every 24h by IV infusion over a 30-minute period, the mean CLT was 9%, 22%, and 46% lower among subjects and patients with mild (CLCR 50–80 mL/min), moderate (CLCR 30–<50 mL/min), and severe (CLCR <30 mL/min) renal impairment, respectively, than in those with normal renal function (CLCR >80 mL/min). The mean steady-state systemic exposure (AUC), t1/2, and Vss increased with decreasing renal function, although the mean AUC for patients with CLCR 30–80 mL/min was not markedly different from the mean AUC for patients with normal renal function. The mean AUC for patients with CLCR <30 mL/min and for patients on dialysis (CAPD and hemodialysis dosed post-dialysis) was approximately 2 and 3 times higher, respectively, than for patients with normal renal function. The mean Cmax ranged from 60 to 70 mcg/mL in patients with CLCR ≥30 mL/min, while the mean Cmax for patients with CLCR <30 mL/min ranged from 41 to 58 mcg/mL. After administration of daptomycin for injection 6 mg/kg every 24h by IV infusion over a 30-minute period, the mean Cmax ranged from 80 to 114 mcg/mL in patients with mild to moderate renal impairment and was similar to that of patients with normal renal function.

Table 12: Mean (SD) Daptomycin Population Pharmacokinetic Parameters Following Infusion of Daptomycin for Injection 4 mg/kg or 6 mg/kg to Infected Adult Patients and Noninfected Adult Subjects with Various Degrees of Renal Function
Renal Function | Pharmacokinetic Parameters [CLCR, creatinine clearance estimated using the Cockcroft-Gault equation with actual body weight; CAPD, continuous ambulatory peritoneal dialysis; AUC0-∞, area under the concentration-time curve extrapolated to infinity; AUCss, area under the concentration-time curve calculated over the 24-hour dosing interval at steady-state; Cmin,ss, trough concentration at steady-state; NA, not applicable.]
Renal Function | t1/2 [Parameters obtained following a single dose from patients with complicated skin and skin structure infections and healthy subjects.] (h) 4 mg/kg | Vss (L/kg) 4 mg/kg | CLT (mL/h/kg) 4 mg/kg | AUC0-∞ (mcg∙h/mL) 4 mg/kg | AUCss [Parameters obtained at steady-state from patients with S. aureus bacteremia.] (mcg∙h/mL) 6 mg/kg | Cmin,ss (mcg/mL) 6 mg/kg
Normal | 9.39 (4.74) | 0.13 (0.05) | 10.9 (4.0) | 417 (155) | 545 (296) | 6.9 (3.5)
(CLCR >80 mL/min) | N=165 | N=165 | N=165 | N=165 | N=62 | N=61
Mild Renal Impairment | 10.75 (8.36) | 0.12 (0.05) | 9.9 (4.0) | 466 (177) | 637 (215) | 12.4 (5.6)
(CLCR 50–80 mL/min) | N=64 | N=64 | N=64 | N=64 | N=29 | N=29
Moderate Renal Impairment | 14.70 (10.50) | 0.15 (0.06) | 8.5 (3.4) | 560 (258) | 868 (349) | 19.0 (9.0)
(CLCR 30–<50 mL/min) | N=24 | N=24 | N=24 | N=24 | N=15 | N=14
Severe Renal Impairment | 27.83 (14.85) | 0.20 (0.15) | 5.9 (3.9) | 925 (467) | 1050 (892) | 24.4 (21.4)
(CLCR <30 mL/min) | N=8 | N=8 | N=8 | N=8 | N=2 | N=2
Hemodialysis | 30.51 (6.51) N=16 | 0.16 (0.04) N=16 | 3.9 (2.1) N=16 | 1193 (399) N=16 | NA | NA
CAPD | 27.56 (4.53) N=5 | 0.11 (0.02) N=5 | 2.9 (0.4) N=5 | 1409 (238) N=5 | NA | NA
Note: Daptomycin for injection was administered over a 30-minute period.

Because renal excretion is the primary route of elimination, adjustment of daptomycin for injection dosage interval is necessary in adult patients with severe renal impairment (CLCR <30 mL/min) [see Dosage and Administration (2.6)].

Patients with Hepatic Impairment

The pharmacokinetics of daptomycin were evaluated in 10 adult subjects with moderate hepatic impairment (Child-Pugh Class B) and compared with those in healthy adult volunteers (N=9) matched for gender, age, and weight. The pharmacokinetics of daptomycin were not altered in subjects with moderate hepatic impairment. No dosage adjustment is warranted when Daptomycin for Injection is administered to patients with mild to moderate hepatic impairment. The pharmacokinetics of daptomycin in patients with severe hepatic impairment (Child-Pugh Class C) have not been evaluated.

Gender

No clinically significant gender-related differences in daptomycin pharmacokinetics have been observed. No dosage adjustment is warranted based on gender when Daptomycin for Injection is administered.

Geriatric Patients

The pharmacokinetics of daptomycin were evaluated in 12 healthy elderly subjects (≥75 years of age) and 11 healthy young adult controls (18 to 30 years of age). Following administration of a single 4 mg/kg dose of daptomycin for injection by IV infusion over a 30-minute period, the mean total clearance of daptomycin was approximately 35% lower and the mean AUC0-∞ was approximately 58% higher in elderly subjects than in healthy young adult subjects. There were no differences in Cmax [see Use in Specific Populations (8.5)].

Obese Patients

The pharmacokinetics of daptomycin were evaluated in 6 moderately obese (Body Mass Index [BMI] 25 to 39.9 kg/m^2) and 6 extremely obese (BMI ≥40 kg/m^2) adult subjects and controls matched for age, gender, and renal function. Following administration of daptomycin for injection by IV infusion over a 30-minute period as a single 4 mg/kg dose based on total body weight, the total plasma clearance of daptomycin normalized to total body weight was approximately 15% lower in moderately obese subjects and 23% lower in extremely obese subjects than in nonobese controls. The AUC0-∞ of daptomycin was approximately 30% higher in moderately obese subjects and 31% higher in extremely obese subjects than in nonobese controls. The differences were most likely due to differences in the renal clearance of daptomycin. No adjustment of Daptomycin for Injection dosage is warranted in obese patients.

Pediatric Patients

The pharmacokinetics of daptomycin in pediatric subjects was evaluated in 3 single-dose pharmacokinetic studies. In general, body weight-normalized total body clearance in pediatric patients was higher than in adults and increased with a decrease of age, whereas elimination half-life tends to decrease with a decrease of age. Body weight-normalized total body clearance and elimination half-life of daptomycin in children 2 to 6 years of age were similar at different doses.

A study was conducted to assess safety, efficacy, and pharmacokinetics of daptomycin in pediatric patients (1 to 17 years old, inclusive) with cSSSI caused by Gram-positive pathogens. Patients were enrolled into 4 age groups [see Clinical Studies (14.1)], and intravenous daptomycin for injection doses of 5 to 10 mg/kg once daily were administered. Following administration of multiple doses, daptomycin exposure (AUCss and Cmax,ss) was similar across different age groups after dose adjustment based on body weight and age (Table 13).

Table 13: Mean (SD) Daptomycin Population Pharmacokinetic Parameters in cSSSI Pediatric Patients
 | Pharmacokinetic Parameters
Age | Dose (mg/kg) | Infusion Duration (min) | AUCss (mcg∙h/mL) | t1/2 (h) | Vss (mL) | CLT (mL/h/kg) | Cmax,ss (mcg/mL)
12 to 17 years (N=6) | 5 | 30 | 434 (67.9) | 7.1 (0.9) | 8200 (3250) | 11.8 (2.15) | 76.4 (6.75)
7 to 11 years (N=2) | 7 | 30 | 543 [Mean is calculated from N=2] | 6.8 | 4470 | 13.2 | 92.4
2 to 6 years (N=7) | 9 | 60 | 452 (93.1) | 4.6 (0.8) | 2750 (832) | 20.8 (4.29) | 90.3 (14.0)
1 to less than 2 years (N=27) | 10 | 60 | 462 (138) | 4.8 (0.6) | 1670 (446) | 23.1 (5.43) | 81.6 (20.7)
AUCss, area under the concentration-time curve at steady state; CLT, clearance normalized to body weight; Vss, volume of distribution at steady state; t½, terminal half-life

A study was conducted to assess safety, efficacy, and pharmacokinetics of daptomycin in pediatric patients with S. aureus bacteremia. Patients were enrolled into 3 age groups [see Clinical Studies (14.2)], and intravenous doses of 7 to 12 mg/kg once daily were administered. Following administration of multiple doses, daptomycin exposure (AUCss and Cmax,ss) was similar across different age groups after dose adjustment based on body weight and age (Table 14).

Table 14: Mean (SD) of Daptomycin Pharmacokinetics in Bacteremia Pediatric Patients
 | Pharmacokinetic Parameters
Age | Dose (mg/kg) | Infusion Duration (min) | AUCss (mcg∙h/mL) | t1/2 (h) | Vss (mL) | CLT (mL/h/kg) | Cmax,ss (mcg/mL)
12 to 17 years (N=13) | 7 | 30 | 656 (334) | 7.5 (2.3) | 6420 (1980) | 12.4 (3.9) | 104 (35.5)
7 to 11 years (N=19) | 9 | 30 | 579 (116) | 6.0 (0.8) | 4510 (1470) | 15.9 (2.8) | 104 (14.5)
2 to 6 years (N=19) | 12 | 60 | 620 (109) | 5.1 (0.6) | 2200 (570) | 19.9 (3.4) | 106 (12.8)
AUCss, area under the concentration-time curve at steady state; CLT, clearance normalized to body weight; Vss, volume of distribution at steady state; t½, terminal half-life
No patients 1 to <2 years of age were enrolled in the study. Simulation using a population pharmacokinetic model demonstrated that the AUCss of daptomycin in pediatric patients 1 to <2 years of age receiving 12 mg/kg once daily would be comparable to that in adult patients receiving 6 mg/kg once daily.

Drug Interaction Studies

In Vitro Studies

In vitro studies with human hepatocytes indicate that daptomycin does not inhibit or induce the activities of the following human cytochrome P450 isoforms: 1A2, 2A6, 2C9, 2C19, 2D6, 2E1, and 3A4. It is unlikely that daptomycin will inhibit or induce the metabolism of drugs metabolized by the P450 system.

Aztreonam

In a study in which 15 healthy adult subjects received a single dose of daptomycin for injection 6 mg/kg IV and a combination dose of Daptomycin for Injection 6 mg/kg IV and aztreonam 1 g IV, administered over a 30-minute period, the Cmax and AUC0-∞ of daptomycin were not significantly altered by aztreonam.

Tobramycin

In a study in which 6 healthy adult males received a single dose of daptomycin for injection 2 mg/kg IV, tobramycin 1 mg/kg IV, and both in combination, administered over a 30-minute period, the mean Cmax and AUC0-∞ of daptomycin were 12.7% and 8.7% higher, respectively, when daptomycin for injection was coadministered with tobramycin. The mean Cmax and AUC0-∞ of tobramycin were 10.7% and 6.6% lower, respectively, when tobramycin was coadministered with daptomycin for injection. These differences were not statistically significant. The interaction between daptomycin and tobramycin with a clinical dose of Daptomycin for Injection is unknown.

Warfarin

In 16 healthy adult subjects, administration of daptomycin for injection 6 mg/kg every 24h by IV infusion over a 30-minute period for 5 days, with coadministration of a single oral dose of warfarin (25 mg) on the 5th day, had no significant effect on the pharmacokinetics of either drug and did not significantly alter the INR (International Normalized Ratio).

Simvastatin

In 20 healthy adult subjects on a stable daily dose of simvastatin 40 mg, administration of daptomycin for injection 4 mg/kg every 24h by IV infusion over a 30-minute period for 14 days (N=10) had no effect on plasma trough concentrations of simvastatin and was not associated with a higher incidence of adverse events, including skeletal myopathy, than in subjects receiving placebo once daily (N=10) [see Warnings and Precautions (5.2) and Drug Interactions (7.1)].

Probenecid

Concomitant administration of probenecid (500 mg 4 times daily) and a single dose of daptomycin for injection 4 mg/kg by IV infusion over a 30-minute period in adults did not significantly alter the Cmax or AUC0-∞ of daptomycin.

12.4 Microbiology

Daptomycin belongs to the cyclic lipopeptide class of antibacterials. Daptomycin has clinical utility in the treatment of infections caused by aerobic, Gram-positive bacteria. The in vitro spectrum of activity of daptomycin encompasses most clinically relevant Gram-positive pathogenic bacteria.

Daptomycin exhibits rapid, concentration-dependent bactericidal activity against Gram-positive bacteria in vitro. This has been demonstrated both by time-kill curves and by MBC/MIC (minimum bactericidal concentration/minimum inhibitory concentration) ratios using broth dilution methodology. Daptomycin maintained bactericidal activity in vitro against stationary phase S. aureus in simulated endocardial vegetations. The clinical significance of this is not known.

Mechanism of Action

Daptomycin binds to bacterial cell membranes and causes a rapid depolarization of membrane potential. This loss of membrane potential causes inhibition of DNA, RNA, and protein synthesis, which results in bacterial cell death.

Resistance

The mechanism(s) of daptomycin resistance is not fully understood. Currently, there are no known transferable elements that confer resistance to daptomycin.

Interactions with Other Antibacterials

In vitro studies have investigated daptomycin interactions with other antibacterials. Antagonism, as determined by kill curve studies, has not been observed. In vitro synergistic interactions of daptomycin with aminoglycosides, β-lactam antibacterials, and rifampin have been shown against some isolates of staphylococci (including some methicillin-resistant isolates) and enterococci (including some vancomycin-resistant isolates).

Complicated Skin and Skin Structure Infection (cSSSI) Trials in Adults

The emergence of daptomycin non-susceptible isolates occurred in 2 infected patients across the set of Phase 2 and pivotal Phase 3 clinical trials of cSSSI in adult patients. In one case, a non-susceptible S. aureus was isolated from a patient in a Phase 2 trial who received daptomycin for injection at less than the protocol-specified dose for the initial 5 days of therapy. In the second case, a non-susceptible Enterococcus faecalis was isolated from a patient with an infected chronic decubitus ulcer who was enrolled in a salvage trial.

S. aureus Bacteremia/Endocarditis and Other Post-Approval Trials in Adults

In subsequent clinical trials in adult patients, non-susceptible isolates were recovered. S. aureus was isolated from a patient in a compassionate-use trial and from 7 patients in the S. aureus bacteremia/endocarditis trial [see Clinical Studies (14.2)]. An E. faecium was isolated from a patient in a vancomycin-resistant enterococci trial.

Antimicrobial Activity

Daptomycin has been shown to be active against most isolates of the following microorganisms both in vitro and in clinical infections [see Indications and Usage (1)].

Gram-Positive Bacteria

Enterococcus faecalis (vancomycin-susceptible isolates only)
Staphylococcus aureus (including methicillin-resistant isolates)
Streptococcus agalactiae
Streptococcus dysgalactiae subsp. equisimilis
Streptococcus pyogenes

The following in vitro data are available, but their clinical significance is unknown. At least 90 percent of the following bacteria exhibit an in vitro minimum inhibitory concentration (MIC) less than or equal to the susceptible breakpoint for daptomycin against isolates of similar genus or organism group. However, the efficacy of daptomycin in treating clinical infections caused by these bacteria has not been established in adequate and well-controlled clinical trials.

Gram-Positive Bacteria

Corynebacterium jeikeium
Enterococcus faecalis (vancomycin-resistant isolates)
Enterococcus faecium (including vancomycin-resistant isolates)
Staphylococcus epidermidis (including methicillin-resistant isolates)
Staphylococcus haemolyticus

Susceptibility Testing

For specific information regarding susceptibility test interpretive criteria and associated test methods and quality control standards recognized by FDA for daptomycin, please see: https://www.fda.gov/STIC.

13 NONCLINICAL TOXICOLOGY

13.1 Carcinogenesis, Mutagenesis, Impairment of Fertility

Long-term carcinogenicity studies in animals have not been conducted to evaluate the carcinogenic potential of daptomycin for injection. However, neither mutagenic nor clastogenic potential was found in a battery of genotoxicity tests, including the Ames assay, a mammalian cell gene mutation assay, a test for chromosomal aberrations in Chinese hamster ovary cells, an in vivo micronucleus assay, an in vitro DNA repair assay, and an in vivo sister chromatid exchange assay in Chinese hamsters.

Daptomycin did not affect the fertility or reproductive performance of male and female rats when administered intravenously at doses of 25, 75, or 150 mg/kg/day, which is approximately up to 9 times the estimated human exposure level based upon AUCs (or approximately up to 4 times the recommended human dose of 6 mg/kg based on body surface area comparison).

13.2 Animal Toxicology and/or Pharmacology

Adult Animals

In animals, daptomycin administration has been associated with effects on skeletal muscle. However, there were no changes in cardiac or smooth muscle. Skeletal muscle effects were characterized by microscopic degenerative/regenerative changes and variable elevations in creatine phosphokinase (CPK). No fibrosis or rhabdomyolysis was evident in repeat-dose studies up to the highest doses tested in rats (150 mg/kg/day) and dogs (100 mg/kg/day). The degree of skeletal myopathy showed no increase when treatment was extended from 1 month to up to 6 months. Severity was dose-dependent. All muscle effects, including microscopic changes, were fully reversible within 30 days following the cessation of dosing.

In adult animals, effects on peripheral nerve (characterized by axonal degeneration and frequently accompanied by significant losses of patellar reflex, gag reflex, and pain perception) were observed at daptomycin doses higher than those associated with skeletal myopathy. Deficits in the dogs' patellar reflexes were seen within 2 weeks after the start of treatment at 40 mg/kg/day (9 times the human Cmax at the 6 mg/kg/day dose), with some clinical improvement noted within 2 weeks after the cessation of dosing. However, at 75 mg/kg/day for 1 month, 7 of 8 dogs failed to regain full patellar reflex responses within a 3-month recovery period. In a separate study in dogs receiving doses of 75 and 100 mg/kg/day for 2 weeks, minimal residual histological changes were noted at 6 months after the cessation of dosing. However, recovery of peripheral nerve function was evident.

Tissue distribution studies in rats showed that daptomycin is retained in the kidney but appears to penetrate the blood-brain barrier only minimally following single and multiple doses.

Juvenile Animals

Target organs of daptomycin-related effects in 7-week-old juvenile dogs were skeletal muscle and nerve, the same target organs as in adult dogs. In juvenile dogs, nerve effects were noted at lower daptomycin blood concentrations than in adult dogs following 28 days of dosing. In contrast to adult dogs, juvenile dogs also showed evidence of effects in nerves of the spinal cord as well as peripheral nerves after 28 days of dosing. No nerve effects were noted in juvenile dogs following 14 days of dosing at doses up to 75 mg/kg/day.

Administration of daptomycin to 7-week-old juvenile dogs for 28 days at doses of 50 mg/kg/day produced minimal degenerative effects on the peripheral nerve and spinal cord in several animals, with no corresponding clinical signs. A dose of 150 mg/kg/day for 28 days produced minimal degeneration in the peripheral nerve and spinal cord as well as minimal to mild degeneration of the skeletal muscle in a majority of animals, accompanied by slight to severe muscle weakness evident in most dogs. Following a 28-day recovery phase, microscopic examination revealed recovery of the skeletal muscle and the ulnar nerve effects, but nerve degeneration in the sciatic nerve and spinal cord was still observed in all 150 mg/kg/day dogs.

Following once-daily administration of daptomycin to juvenile dogs for 28 days, microscopic effects in nerve tissue were noted at a Cmax value of 417 mcg/mL, which is approximately 3-fold less than the Cmax value associated with nerve effects in adult dogs treated once daily with daptomycin for 28 days (1308 mcg/mL).

Neonatal Animals

Neonatal dogs (4 to 31 days old) were more sensitive to daptomycin-related adverse nervous system and/or muscular system effects than either juvenile or adult dogs. In neonatal dogs, adverse nervous system and/or muscular system effects were associated with a Cmax value approximately 3-fold less than the Cmax in juvenile dogs, and 9-fold less than the Cmax in adult dogs following 28 days of dosing. At a dose of 25 mg/kg/day with associated Cmax and AUCinf values of 147 mcg/mL and 717 mcg∙h/mL, respectively (1.6 and 1.0-fold the adult human Cmax and AUC, respectively, at the 6 mg/kg/day dose), mild clinical signs of twitching and one incidence of muscle rigidity were observed with no corresponding effect on body weight. These effects were found to be reversible within 28 days after treatment had stopped.

At higher dose levels of 50 and 75 mg/kg/day with associated Cmax and AUCinf values of ≥321 mcg/mL and ≥1470 mcg∙h/mL, respectively, marked clinical signs of twitching, muscle rigidity in the limbs, and impaired use of limbs were observed. Resulting decreases in body weights and overall body condition at doses ≥50 mg/kg/day necessitated early discontinuation by postnatal day (PND) 19.

Histopathological assessment did not reveal any daptomycin-related changes in the peripheral and central nervous system tissue, as well as in the skeletal muscle or other tissues assessed, at any dose level.

No adverse effects were observed in the dogs that received daptomycin at 10 mg/kg/day, the NOAEL, with associated Cmax and AUCinf values of 62 mcg/mL and 247 mcg∙h/mL, respectively (or 0.6 and 0.4-fold the adult human Cmax and AUC, respectively at the 6 mg/kg dose).

14 CLINICAL STUDIES

14.1 Complicated Skin and Skin Structure Infections

Adults with cSSSI

Adult patients with clinically documented complicated skin and skin structure infections (cSSSI) (Table 15) were enrolled in two randomized, multinational, multicenter, investigator-blinded trials comparing daptomycin for injection (4 mg/kg IV every 24h) with either vancomycin (1 g IV q12h) or an anti-staphylococcal semi-synthetic penicillin (i.e., nafcillin, oxacillin, cloxacillin, or flucloxacillin; 4 to 12 g IV per day). Patients could switch to oral therapy after a minimum of 4 days of IV treatment if clinical improvement was demonstrated. Patients known to have bacteremia at baseline were excluded. Patients with creatinine clearance (CLCR) between 30 and 70 mL/min were to receive a lower dose of daptomycin for injection as specified in the protocol; however, the majority of patients in this subpopulation did not have the dose of daptomycin for injection adjusted.

Table 15: Investigator's Primary Diagnosis in the cSSSI Trials in Adult Patients (Population: ITT)
Primary Diagnosis | Adult Patients (Daptomycin for Injection / Comparator [Comparator: vancomycin (1 g IV q12h) or an anti-staphylococcal semi-synthetic penicillin (i.e., nafcillin, oxacillin, cloxacillin, or flucloxacillin; 4 to 12 g/day IV in divided doses).])
Primary Diagnosis | Study 9801 N=264 / N=266 | Study 9901 N=270 / N=292 | Pooled N=534 / N=558
Wound Infection | 99 (38%) / 116 (44%) | 102 (38%) / 108 (37%) | 201 (38%) / 224 (40%)
Major Abscess | 55 (21%) / 43 (16%) | 59 (22%) / 65 (22%) | 114 (21%) / 108 (19%)
Ulcer Infection | 71 (27%) / 75 (28%) | 53 (20%) / 68 (23%) | 124 (23%) / 143 (26%)
Other Infection [The majority of cases were subsequently categorized as complicated cellulitis, major abscesses, or traumatic wound infections.] | 39 (15%) / 32 (12%) | 56 (21%) / 51 (18%) | 95 (18%) / 83 (15%)

One trial was conducted primarily in the United States and South Africa (study 9801), and the second was conducted at non-US sites only (study 9901). The two trials were similar in design but differed in patient characteristics, including history of diabetes and peripheral vascular disease. There were a total of 534 adult patients treated with daptomycin for injection and 558 treated with comparator in the two trials. The majority (89.7%) of patients received IV medication exclusively.

The efficacy endpoints in both trials were the clinical success rates in the intent-to-treat (ITT) population and in the clinically evaluable (CE) population. In study 9801, clinical success rates in the ITT population were 62.5% (165/264) in patients treated with daptomycin for injection and 60.9% (162/266) in patients treated with comparator drugs. Clinical success rates in the CE population were 76.0% (158/208) in patients treated with daptomycin for injection and 76.7% (158/206) in patients treated with comparator drugs. In study 9901, clinical success rates in the ITT population were 80.4% (217/270) in patients treated with daptomycin for injection and 80.5% (235/292) in patients treated with comparator drugs. Clinical success rates in the CE population were 89.9% (214/238) in patients treated with daptomycin for injection and 90.4% (226/250) in patients treated with comparator drugs.

The success rates by pathogen for microbiologically evaluable patients are presented in Table 16.

Table 16: Clinical Success Rates by Infecting Pathogen in the cSSSI Trials in Adult Patients (Population: Microbiologically Evaluable)
Pathogen | Success Rate n/N (%)
Pathogen | Daptomycin for Injection | Comparator [Comparator: vancomycin (1 g IV q12h) or an anti-staphylococcal semi-synthetic penicillin (i.e., nafcillin, oxacillin, cloxacillin, or flucloxacillin; 4 to 12 g/day IV in divided doses).]
Methicillin-susceptible Staphylococcus aureus (MSSA) [As determined by the central laboratory.] | 170/198 (86%) | 180/207 (87%)
Methicillin-resistant Staphylococcus aureus (MRSA) | 21/28 (75%) | 25/36 (69%)
Streptococcus pyogenes | 79/84 (94%) | 80/88 (91%)
Streptococcus agalactiae | 23/27 (85%) | 22/29 (76%)
Streptococcus dysgalactiae subsp. equisimilis | 8/8 (100%) | 9/11 (82%)
Enterococcus faecalis (vancomycin-susceptible only) | 27/37 (73%) | 40/53 (76%)

Pediatric Patients (1 to 17 Years of Age) with cSSSI

The cSSSI pediatric trial was a single prospective multi-center, randomized, comparative trial. A total of 396 pediatric patients aged 1 to 17 years with cSSSI caused by Gram positive pathogens were enrolled into the study. Patients known to have bacteremia, osteomyelitis, endocarditis, and pneumonia at baseline were excluded. Patients were enrolled in a stepwise approach into four age groups and given age-dependent doses of daptomycin for injection once daily for up to 14 days. The different age groups and doses evaluated were as follows: Adolescents (12 to 17 years) treated with 5 mg/kg of daptomycin for injection (n=113), Children (7 to 11 years) treated with 7 mg/kg of daptomycin for injection (n=113), Children (2 to 6 years) treated with 9 mg/kg of daptomycin for injection (n=125) and Infants (1 to <2 years) treated with 10 mg/kg (n= 45).

Patients were randomized 2:1 to receive daptomycin for injection or a standard of care (SOC) comparator, which included intravenous therapy with either vancomycin, clindamycin, or an anti-staphylococcal semi-synthetic penicillin (nafcillin, oxacillin, or cloxacillin). Patients could switch to oral therapy after clinical improvement was demonstrated (no minimum IV dosing was required).

The primary objective of this study was to evaluate the safety of daptomycin for injection. The clinical outcome was determined by resolution or improvement of symptoms at the End-of-Treatment (EOT), 3 days after the last dose, and Test-of-Cure (TOC), 7-14 days after the last dose. Investigator observed outcomes were verified in a blinded fashion. Of the 396 subjects randomized in the study, 389 subjects were treated with daptomycin for injection or comparator and included in the ITT population. Of these, 257 subjects were randomized to the daptomycin for injection group and 132 subjects were randomized to the comparator group. Approximately 95% of subjects switched to oral therapy. The mean day of switch was day 4, and ranged from day 1 to day 14. The clinical success rates determined at 7-14 days after last dose of therapy (IV and oral) (TOC visit) were 88% (227/257) for daptomycin for injection and 86% (114/132) for comparator.

14.2 S. aureus Bacteremia/Endocarditis

Adults with S. aureus Bacteremia/Endocarditis

The efficacy of daptomycin for injection in the treatment of adult patients with S. aureus bacteremia was demonstrated in a randomized, controlled, multinational, multicenter, open-label trial. In this trial, adult patients with at least one positive blood culture for S. aureus obtained within 2 calendar days prior to the first dose of study drug and irrespective of source were enrolled and randomized to either daptomycin for injection (6 mg/kg IV every 24h) or standard of care [an anti-staphylococcal semi-synthetic penicillin 2 g IV q4h (nafcillin, oxacillin, cloxacillin, or flucloxacillin) or vancomycin 1 g IV q12h, each with initial gentamicin 1 mg/kg IV every 8 hours for first 4 days]. Of the patients in the comparator group, 93% received initial gentamicin for a median of 4 days, compared with 1 patient (<1%) in the daptomycin for injection group. Patients with prosthetic heart valves, intravascular foreign material that was not planned for removal within 4 days after the first dose of study medication, severe neutropenia, known osteomyelitis, polymicrobial bloodstream infections, creatinine clearance <30 mL/min, and pneumonia were excluded.

Upon entry, patients were classified for likelihood of endocarditis using the modified Duke criteria (Possible, Definite, or Not Endocarditis). Echocardiography, including a transesophageal echocardiogram (TEE), was performed within 5 days following study enrollment. The choice of comparator agent was based on the oxacillin susceptibility of the S. aureus isolate. The duration of study treatment was based on the investigator's clinical diagnosis. Final diagnoses and outcome assessments at Test of Cure (6 weeks after the last treatment dose) were made by a treatment-blinded Adjudication Committee, using protocol-specified clinical definitions and a composite primary efficacy endpoint (clinical and microbiological success) at the Test of Cure visit.

A total of 246 patients ≥18 years of age (124 daptomycin for injection, 122 comparator) with S. aureus bacteremia were randomized from 48 centers in the US and Europe. In the ITT population, 120 patients received daptomycin for injection and 115 received comparator (62 received an anti-staphylococcal semi-synthetic penicillin and 53 received vancomycin). Thirty-five patients treated with an anti-staphylococcal semi-synthetic penicillin received vancomycin initially for 1 to 3 days, pending final susceptibility results for the S. aureus isolates. The median age among the 235 patients in the ITT population was 53 years (range: 21 to 91 years); 30/120 (25%) in the daptomycin for injection group and 37/115 (32%) in the comparator group were ≥65 years of age. Of the 235 ITT patients, there were 141 (60%) males and 156 (66%) Caucasians across the two treatment groups. In addition, 176 (75%) of the ITT population had systemic inflammatory response syndrome (SIRS) at baseline and 85 (36%) had surgical procedures within 30 days prior to onset of the S. aureus bacteremia. Eighty-nine patients (38%) had bacteremia caused by methicillin-resistant S. aureus (MRSA). Entry diagnosis was based on the modified Duke criteria and comprised 37 (16%) Definite, 144 (61%) Possible, and 54 (23%) Not Endocarditis. Of the 37 patients with an entry diagnosis of Definite Endocarditis, all (100%) had a final diagnosis of infective endocarditis, and of the 144 patients with an entry diagnosis of Possible Endocarditis, 15 (10%) had a final diagnosis of infective endocarditis as assessed by the Adjudication Committee. Of the 54 patients with an entry diagnosis of Not Endocarditis, 1 (2%) had a final diagnosis of infective endocarditis as assessed by the Adjudication Committee.

In the ITT population, there were 182 patients with bacteremia and 53 patients with infective endocarditis as assessed by the Adjudication Committee, including 35 with right-sided endocarditis and 18 with left-sided endocarditis. The 182 patients with bacteremia comprised 121 with complicated S. aureus bacteremia and 61 with uncomplicated S. aureus bacteremia.

Complicated bacteremia was defined as S. aureus isolated from blood cultures obtained on at least 2 different calendar days, and/or metastatic foci of infection (deep tissue involvement), and classification of the patient as not having endocarditis according to the modified Duke criteria. Uncomplicated bacteremia was defined as S. aureus isolated from blood culture(s) obtained on a single calendar day, no metastatic foci of infection, no infection of prosthetic material, and classification of the patient as not having endocarditis according to the modified Duke criteria. The definition of right-sided infective endocarditis (RIE) used in the clinical trial was Definite or Possible Endocarditis according to the modified Duke criteria and no echocardiographic evidence of predisposing pathology or active involvement of either the mitral or aortic valve. Complicated RIE comprised patients who were not intravenous drug users, had a positive blood culture for MRSA, serum creatinine ≥2.5 mg/dL, or evidence of extrapulmonary sites of infection. Patients who were intravenous drug users, had a positive blood culture for methicillin-susceptible S. aureus (MSSA), had serum creatinine <2.5 mg/dL, and were without evidence of extrapulmonary sites of infection were considered to have uncomplicated RIE.

The coprimary efficacy endpoints in the trial were the Adjudication Committee success rates at the Test of Cure visit (6 weeks after the last treatment dose) in the ITT and Per Protocol (PP) populations. The overall Adjudication Committee success rates in the ITT population were 44.2% (53/120) in patients treated with daptomycin for injection and 41.7% (48/115) in patients treated with comparator (difference = 2.4% [95% CI −10.2, 15.1]). The success rates in the PP population were 54.4% (43/79) in patients treated with daptomycin for injection and 53.3% (32/60) in patients treated with comparator (difference = 1.1% [95% CI −15.6, 17.8]).

Adjudication Committee success rates are shown in Table 17.

Table 17: Adjudication Committee Success Rates at Test of Cure in the S. aureus Bacteremia/Endocarditis Trial in Adult Patients (Population: ITT)
Population | Success Rate n/N (%) |  | Difference: Daptomycin for Injection − Comparator (Confidence Interval)
Population | Daptomycin for Injection 6 mg/kg | Comparator [Comparator: vancomycin (1 g IV q12h) or an anti-staphylococcal semi-synthetic penicillin (i.e., nafcillin, oxacillin, cloxacillin, or flucloxacillin; 2 g IV q4h), each with initial low-dose gentamicin.] | Difference: Daptomycin for Injection − Comparator (Confidence Interval)
Overall | 53/120 (44%) | 48/115 (42%) | 2.4% (−10.2, 15.1) [95% Confidence Interval]
Baseline Pathogen
Methicillin-susceptible S. aureus | 33/74 (45%) | 34/70 (49%) | −4.0% (−22.6, 14.6) [97.5% Confidence Interval (adjusted for multiplicity)]
Methicillin-resistant S. aureus | 20/45 (44%) | 14/44 (32%) | 12.6% (−10.2, 35.5)
Entry Diagnosis [According to the modified Duke criteria^5]
Definite or Possible Infective Endocarditis | 41/90 (46%) | 37/91 (41%) | 4.9% (−11.6, 21.4)
Not Infective Endocarditis | 12/30 (40%) | 11/24 (46%) | −5.8% (−36.2, 24.5)
Final Diagnosis
Uncomplicated Bacteremia | 18/32 (56%) | 16/29 (55%) | 1.1% (−31.7, 33.9) [99% Confidence Interval (adjusted for multiplicity)]
Complicated Bacteremia | 26/60 (43%) | 23/61 (38%) | 5.6% (−17.3, 28.6)
Right-Sided Infective Endocarditis | 8/19 (42%) | 7/16 (44%) | −1.6% (−44.9, 41.6)
Uncomplicated Right-Sided Infective Endocarditis | 3/6 (50%) | 1/4 (25%) | 25.0% (−51.6, 100.0)
Complicated Right-Sided Infective Endocarditis | 5/13 (39%) | 6/12 (50%) | −11.5% (−62.4, 39.4)
Left-Sided Infective Endocarditis | 1/9 (11%) | 2/9 (22%) | −11.1% (−55.9, 33.6)

Eighteen (18/120) patients in the daptomycin for injection arm and 19/116 patients in the comparator arm died during the trial. These comprise 3/28 daptomycin for injection-treated patients and 8/26 comparator-treated patients with endocarditis, as well as 15/92 daptomycin for injection-treated patients and 11/90 comparator-treated patients with bacteremia. Among patients with persisting or relapsing S. aureus infections, 8/19 daptomycin for injection-treated patients and 7/11 comparator-treated patients died.

Overall, there was no difference in time to clearance of S. aureus bacteremia between daptomycin for injection and comparator. The median time to clearance in patients with MSSA was 4 days and in patients with MRSA was 8 days.

Failure of treatment due to persisting or relapsing S. aureus infections was assessed by the Adjudication Committee in 19/120 (16%) daptomycin for injection-treated patients (12 with MRSA and 7 with MSSA) and 11/115 (10%) comparator-treated patients (9 with MRSA treated with vancomycin and 2 with MSSA treated with an anti-staphylococcal semi-synthetic penicillin). Among all failures, isolates from 6 daptomycin for injection-treated patients and 1 vancomycin-treated patient developed increasing MICs (reduced susceptibility) by central laboratory testing during or following therapy. Most patients who failed due to persisting or relapsing S. aureus infection had deep-seated infection and did not receive necessary surgical intervention [see Warnings and Precautions (5.9)].

Pediatric Patients (1 to 17 Years of Age) with S. aureus Bacteremia

The pediatric S. aureus bacteremia study was designed as a prospective multi-center, randomized, comparative trial to treat pediatric patients aged 1 to 17 years with bacteremia. Patients known to have endocarditis or pneumonia at baseline were excluded. Patients were enrolled in a stepwise approach into three age groups and given age-dependent doses of daptomycin for injection once daily for up to 42 days. The different age groups and doses evaluated were as follows: Adolescents (12 to 17 years, n=14 patients) treated with daptomycin for injection dosed at 7 mg/kg once daily, Children (7 to 11 years, n=19 patients) treated with daptomycin for injection dosed at 9 mg/kg once daily and Children (2 to 6 years, n=22 patients) treated with daptomycin for injection dosed at 12 mg/kg once daily. No patients 1 to <2 years of age were enrolled.

Patients were randomized 2:1 to receive daptomycin for injection or a standard of care comparator, which included intravenous therapy with vancomycin, semi-synthetic penicillin, first generation cephalosporin or clindamycin. Patients could switch to oral therapy after clinical improvement was demonstrated (no minimum IV dosing was required).

The primary objective of this study was to assess the safety of daptomycin for injection. The clinical outcome was determined by resolution or improvement of symptoms at test-of-cure (TOC) visit, 7 to 14 days after the last dose, which was assessed by the site level Blinded Evaluator.

Of the 82 subjects randomized in the study, 81 subjects were treated with daptomycin for injection or comparator and included in the safety population, and 73 had a proven S. aureus bacteremia at Baseline. Of these, 51 subjects were randomized to the daptomycin for injection group and 22 subjects were randomized to the comparator group. The mean duration of IV therapy was 12 days, with a range of 1 to 44 days. Forty-eight subjects switched to oral therapy, and the mean duration of oral therapy was 21 days. The clinical success rates determined at 7 to 14 days after last dose of therapy (IV and oral) (TOC visit) were 88% (45/51) for daptomycin for injection and 77% (17/22) for comparator.

15 REFERENCES

1. Liu SL, Howard LC, Van Lier RBL, Markham JK: Teratology studies with daptomycin administered intravenously (iv) to rats and rabbits. Teratology 37(5):475, 1988.
2. Stroup JS, Wagner J, Badzinski T: Use of daptomycin in a pregnant patient with Staphylococcus aureus endocarditis. Ann Pharmacother 44(4):746-749, 2010.
3. Buitrago MI, Crompton JA, Bertolami S, North DS, Nathan RA. Extremely low excretion of daptomycin into breast milk of a nursing mother with methicillin-resistant Staphylococcus aureus pelvic inflammatory disease. Pharmacotherapy 2009;29(3):347–351.
4. Klibanov OM, Vickery S, Nortey C: Successful treatment of infective panniculitis with daptomycin in a pregnant, morbidly obese patient. Ann Pharmacother 48(5):652-655, 2014.
5. Li JS, Sexton DJ, Mick N, Nettles R, Fowler VG Jr, Ryan T, Bashore T, Corey GR. Proposed modifications to the Duke criteria for the diagnosis of infective endocarditis. Clin Infect Dis 2000;30:633–638.

16 HOW SUPPLIED/STORAGE AND HANDLING

Daptomycin for Injection is supplied as a sterile pale yellow to light brown lyophilized cake in a single-dose 15 mL vial containing 350 mg of daptomycin: Package of 1 (NDC 0143-9455-01).

STORAGE AND HANDLING

Store original packages at refrigerated temperatures, 2°C to 8°C (36°F to 46°F); avoid excessive heat. Storage conditions for the reconstituted and diluted solutions are described in another section of the prescribing information [see Dosage and Administration (2.7)].

17 PATIENT COUNSELING INFORMATION

Allergic Reactions

Advise patients that allergic reactions, including serious skin, kidney, lung, or other organ reactions, could occur and that these serious reactions require immediate treatment. Patients should report any previous allergic reactions to daptomycin [see Warnings and Precautions (5.1, 5.4, 5.5)].

Muscle Pain or Weakness (Myopathy and Rhabdomyolysis, Peripheral Neuropathy)

Advise patients to report muscle pain or weakness, especially in the forearms and lower legs, as well as tingling or numbness [see Warnings and Precautions (5.2, 5.6)].

Cough, Breathlessness, or Fever (Eosinophilic Pneumonia)

Advise patients to report any symptoms of cough, breathlessness, or fever [see Warnings and Precautions (5.3)].

C. difficile-Associated Diarrhea (CDAD)

Advise patients that diarrhea is a common problem caused by antibacterials, including daptomycin for injection, that usually ends when the antibacterial is discontinued. Sometimes after starting treatment with antibacterials, including Daptomycin for Injection, patients can develop watery and bloody stools (with or without stomach cramps and fever), even as late as 2 or more months after having received the last dose of the antibacterial. If this occurs, patients should contact their physician as soon as possible [see Warnings and Precautions (5.8)].

Antibacterial Resistance Patients should be counseled that antibacterial drugs, including Daptomycin for Injection, should be used to treat bacterial infections. They do not treat viral infections (e.g., the common cold). When Daptomycin for Injection is prescribed to treat a bacterial infection, patients should be told that although it is common to feel better early in the course of therapy, the medication should be taken exactly as directed. Skipping doses or not completing the full course of therapy may (1) decrease the effectiveness of the immediate treatment and (2) increase the likelihood that bacteria will develop resistance and will not be treatable by Daptomycin for Injection or other antibacterial drugs in the future.

Manufactured for:

Hikma Pharmaceuticals USA Inc.
Berkeley Heights, NJ 07922
Made in India

1313001200-00

PRINCIPAL DISPLAY PANEL - 350 mg Vial Carton

NDC 0143-9455-01

Rx Only

For Intravenous Infusion.

Daptomycin
for Injection

350 mg/vial

MUST BE REFRIGERATED

Use 0.9% Sodium Chloride
Injection for reconstitution only.

One Single-Dose Vial

Discard Unused Portion